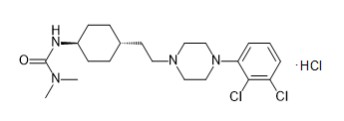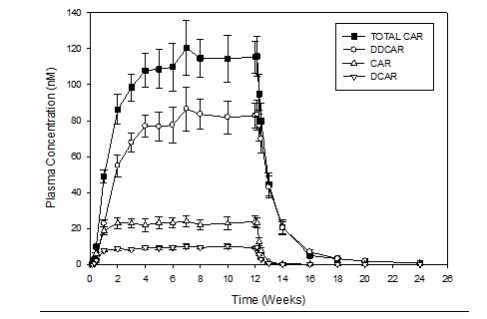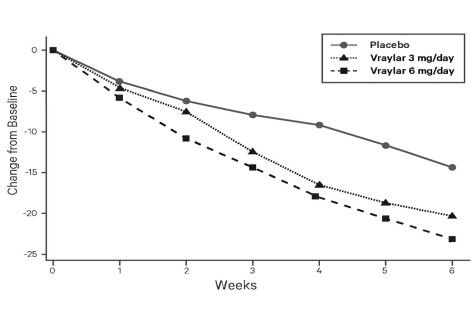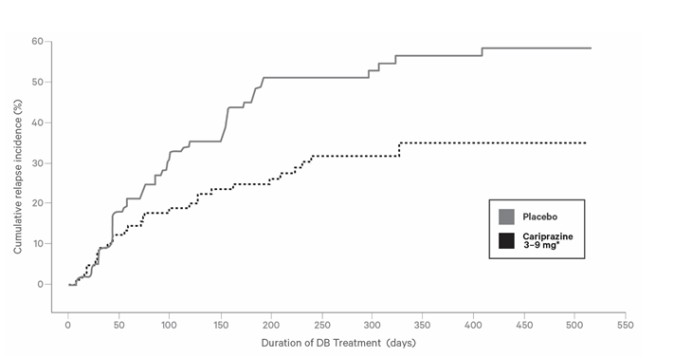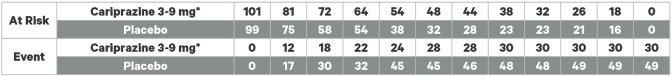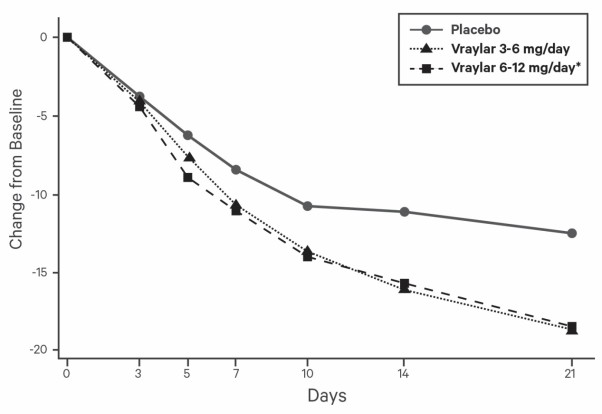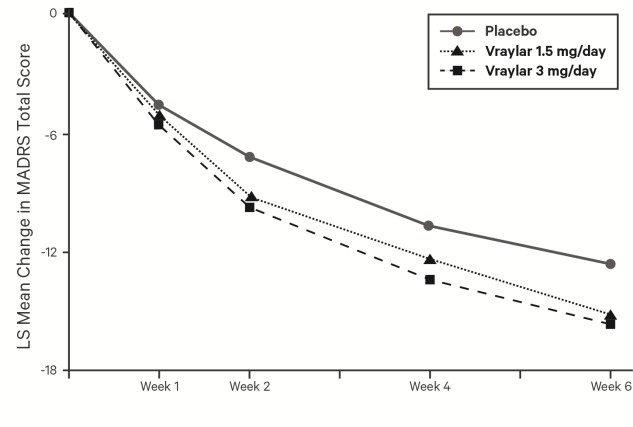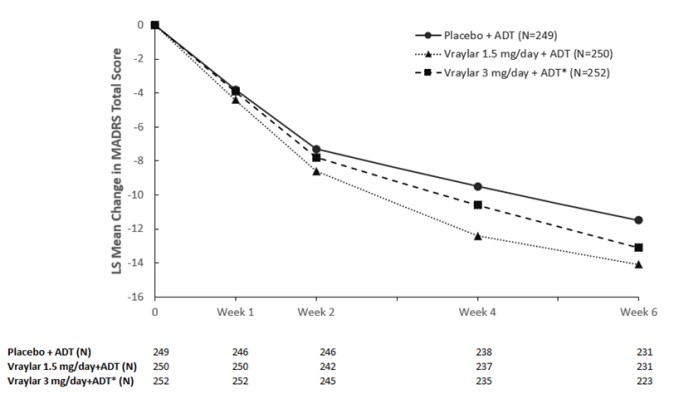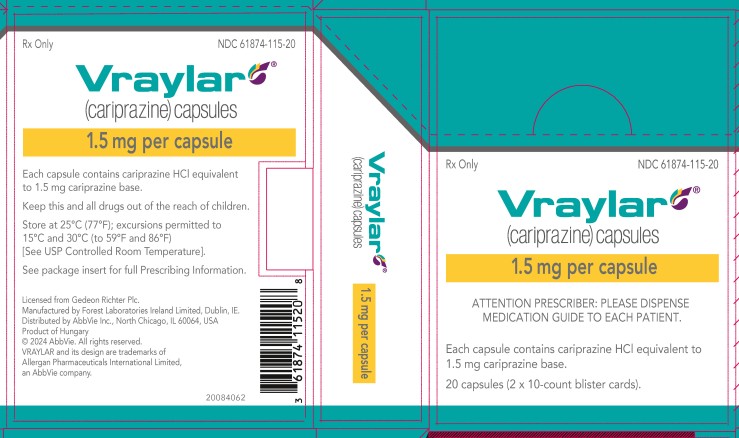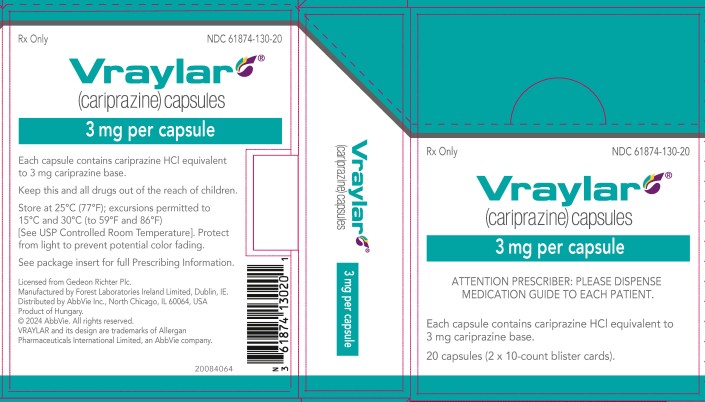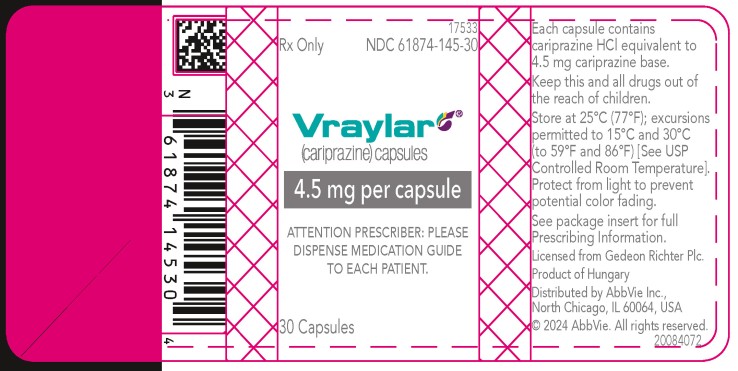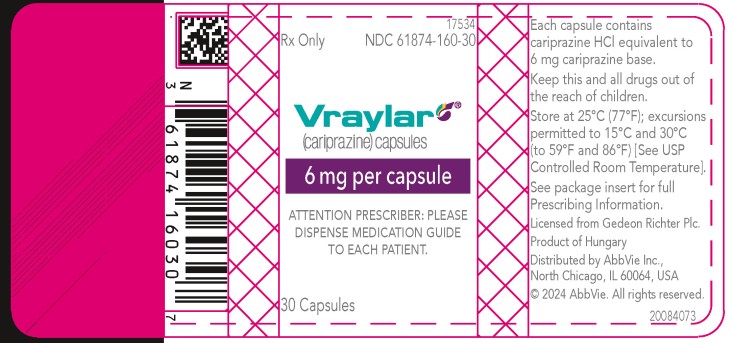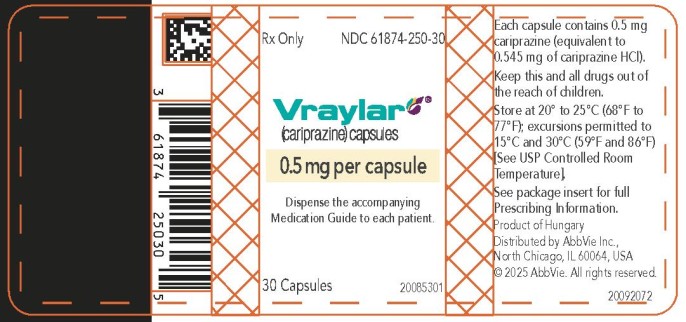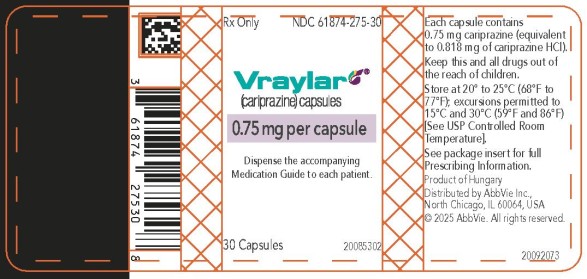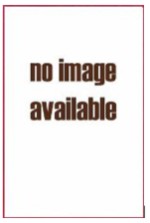 DRUG LABEL: Vraylar
NDC: 61874-250 | Form: CAPSULE, GELATIN COATED
Manufacturer: Allergan, Inc.
Category: prescription | Type: HUMAN PRESCRIPTION DRUG LABEL
Date: 20251218

ACTIVE INGREDIENTS: CARIPRAZINE 0.5 mg/1 1
INACTIVE INGREDIENTS: GELATIN, UNSPECIFIED; MAGNESIUM STEARATE; STARCH, CORN; SHELLAC; TITANIUM DIOXIDE; FERROSOFERRIC OXIDE; FD&C BLUE NO. 1; FERRIC OXIDE YELLOW

HIGHLIGHTS OF PRESCRIBING INFORMATION

These highlights do not include all the information needed to use VRAYLAR safely and effectively. See full prescribing information for VRAYLAR.
VRAYLAR® (cariprazine) capsules, for oral use
Initial U.S. Approval: 2015

RECENT MAJOR CHANGES

Indications and Usage (1) | 12/2025
Dosage and Administration (2.2, 2.3, 2.6) | 12/2025
Warnings and Precautions, Metabolic Changes (5.7) | 12/2025

WARNING: INCREASED MORTALITY IN ELDERLY PATIENTS WITH DEMENTIA-RELATED PSYCHOSIS and SUICIDAL THOUGHTS AND BEHAVIORS

See full prescribing information for complete boxed warning.

- Elderly patients with dementia-related psychosis treated with antipsychotic drugs are at an increased risk of death. VRAYLAR is not approved for the treatment of patients with dementia-related psychosis. (5.1)
- Antidepressants increased the risk of suicidal thoughts and behaviors in pediatric and young adult patients. Closely monitor all antidepressant-treated patients for clinical worsening and emergence of suicidal thoughts and behaviors. (5.2)

1. INDICATIONS AND USAGE

VRAYLAR is an atypical antipsychotic indicated for:

- Treatment of schizophrenia in adults and pediatric patients 13 years of age and older (1)
- Acute treatment of manic or mixed episodes associated with bipolar I disorder in adults and pediatric patients 10 years of age and older (1)
- Treatment of depressive episodes associated with bipolar I disorder (bipolar depression) in adults (1)
- Adjunctive therapy to antidepressants for the treatment of major depressive disorder (MDD) in adults (1)

2. DOSAGE AND ADMINISTRATION

- Administer VRAYLAR orally once daily with or without food (2)

 | Starting Dose | Recommended Dose
Schizophrenia in Adults (2.2) | 1.5 mg daily | 1.5 mg to 6 mg daily
Schizophrenia in Pediatric Patients (13-17 years) (2.2) | 0.5 mg daily | 1.5 mg to 4.5 mg daily
Bipolar Mania in Adults (2.3) | 1.5 mg daily | 3 mg to 6 mg daily
Bipolar Mania in Pediatric Patients (10-17 years) (2.3) | 0.5 mg daily | 3 mg or 4.5 mg daily
Bipolar Depression in Adults (2.4) | 1.5 mg daily | 1.5 mg or 3 mg daily
Adjunctive therapy to antidepressants for MDD in Adults (2.5) | 1.5 mg daily | 1.5 mg or 3 mg daily

- Adults with Schizophrenia and Bipolar Mania: Maximum recommended daily dosage is 6 mg. Dosages above 6 mg daily do not confer significant benefit, but increase the risk of dose-related adverse reactions (2.2, 2.3)
- Pediatric patients with Schizophrenia and Bipolar Mania: Maximum recommended daily dosage is 4.5 mg.
- Adults with Bipolar Depression: Maximum recommended daily dosage is 3 mg (2.4)
- Adjunctive therapy for treatment of MDD in Adults: Maximum recommended daily dosage is 3 mg (2.5)

3. DOSAGE FORMS AND STRENGTHS

Capsules: 0.5 mg, 0.75 mg, 1.5 mg, 3 mg, 4.5 mg, and 6 mg (3)

4. CONTRAINDICATIONS

- Known hypersensitivity to VRAYLAR (4)

5. WARNINGS AND PRECAUTIONS

- Cerebrovascular Adverse Reactions in Elderly Patients with Dementia-Related Psychosis: Increased incidence of cerebrovascular adverse reactions (e.g., stroke, transient ischemic attack) (5.3)
- Neuroleptic Malignant Syndrome: Manage with immediate discontinuation and close monitoring (5.4)
- Tardive Dyskinesia: Discontinue if appropriate (5.5)
- Late-Occurring Adverse Reactions: Because of VRAYLAR’s long half-life, monitor for adverse reactions and patient response for several weeks after starting VRAYLAR and with each dosage change (5.6)
- Metabolic Changes: Monitor for hyperglycemia/diabetes mellitus, dyslipidemia and weight gain (5.7)
- Leukopenia, Neutropenia, and Agranulocytosis: Perform complete blood counts (CBC) in patients with pre-existing low white blood cell counts (WBC) or history of leukopenia or neutropenia. Consider discontinuing VRAYLAR if a clinically significant decline in WBC occurs in absence of other causative factors (5.8)
- Orthostatic Hypotension and Syncope: Monitor heart rate and blood pressure and warn patients with known cardiovascular or cerebrovascular disease, and risk of dehydration or syncope (5.9)
- Seizures: Use cautiously in patients with a history of seizures or with conditions that lower the seizure threshold (5.11)
- Potential for Cognitive and Motor Impairment: Use caution when operating machinery (5.12)

6 ADVERSE REACTIONS

Most common adverse reactions in adults (incidence ≥ 5% and at least twice the rate of placebo) were (6.1):

- Schizophrenia: extrapyramidal symptoms and akathisia
- Bipolar mania: extrapyramidal symptoms, akathisia, dyspepsia, vomiting, somnolence, and restlessness
- Bipolar depression: nausea, akathisia, restlessness, and extrapyramidal symptoms
- Adjunctive treatment of MDD: akathisia, restlessness, fatigue, constipation, nausea, insomnia, increased appetite, dizziness, and extrapyramidal symptoms

To report SUSPECTED ADVERSE REACTIONS, contact AbbVie at 1-800-633-9110 or FDA at 1-800-FDA-1088 or www.fda.gov/medwatch.

7 DRUG INTERACTIONS

- Strong and Moderate CYP3A4 inhibitors: Reduce VRAYLAR dosage (2.6, 7)
- CYP3A4 inducers: Concomitant use is not recommended (2.6, 7)

8 USE IN SPECIFIC POPULATIONS

- Pregnancy: Based on animal data, may cause fetal harm. (8.1)

FULL PRESCRIBING INFORMATION

WARNING: INCREASED MORTALITY IN ELDERLY PATIENTS WITH DEMENTIA-RELATED PSYCHOSIS and SUICIDAL THOUGHTS AND BEHAVIORS

Increased Mortality in Elderly Patients with Dementia-Related Psychosis

Elderly patients with dementia-related psychosis treated with antipsychotic drugs are at an increased risk of death. VRAYLAR is not approved for the treatment of patients with dementia-related psychosis [see Warnings and Precautions (5.1)].

Suicidal Thoughts and Behaviors

Antidepressants increased the risk of suicidal thoughts and behaviors in pediatric and young adult patients in short-term studies. Closely monitor all antidepressant-treated patients for clinical worsening, and for the emergence of suicidal thoughts and behaviors [see Warnings and Precautions (5.2)].

1. INDICATIONS AND USAGE

VRAYLAR® is indicated for:

• Treatment of schizophrenia in adult and pediatric patients 13 years of age and older [see Clinical Studies (14.1)]

• Acute treatment of manic or mixed episodes associated with bipolar I disorder in adult and pediatric patients 10 years of age and older [see Clinical Studies (14.2)]

• Treatment of depressive episodes associated with bipolar I disorder (bipolar depression) in adult patients [see Clinical Studies (14.3)]

• Adjunctive therapy to antidepressants for the treatment of major depressive disorder (MDD) in adult patients [see Clinical Studies (14.4)]

2. DOSAGE AND ADMINISTRATION

2.1 General Dosing Information

VRAYLAR is given orally once daily and can be taken with or without food.

Because of the long half-life of cariprazine and its active metabolites, changes in dose will not be fully reflected in plasma for several weeks. Prescribers should monitor patients for adverse reactions and treatment response for several weeks after starting VRAYLAR and after each dosage change [see Warnings and Precautions (5.6), Clinical Pharmacology (12.3)].

2.2 Recommended Dosage in Schizophrenia

Adult Patients

The starting dosage of VRAYLAR is 1.5 mg orally once daily. The recommended dosage range is 1.5 mg to 6 mg orally once daily. The dosage can be increased to 3 mg on Day 2. Depending upon clinical response and tolerability, further dose adjustments can be made in 1.5 mg or 3 mg increments. The maximum recommended dosage is 6 mg orally once daily. In short-term controlled trials, dosages above 6 mg daily do not confer increased effectiveness sufficient to outweigh dose-related adverse reactions [see Adverse Reactions (6.1), Clinical Studies (14.1)].

Pediatric Patients (13 to 17 years of age)

The starting dosage of VRAYLAR is 0.5 mg orally once daily. The recommended dosage range is 1.5 mg to 4.5 mg orally once daily. Increase the dosage to 1.5 mg orally once daily on Day 3. Depending upon clinical response and tolerability, the dosage may be increased to 3 mg orally once daily starting on Day 5, and to 4.5 mg orally once daily starting on Day 8. The maximum recommended dosage is 4.5 mg orally once daily.

2.3 Recommended Dosage in Manic or Mixed Episodes Associated with Bipolar I Disorder

Adult Patients

The starting dosage of VRAYLAR is 1.5 mg orally once daily. Increase the dosage to 3 mg orally once daily on Day 2. The recommended dosage range is 3 mg to 6 mg orally once daily. Depending upon clinical response and tolerability, further dose adjustments can be made in 1.5 mg or 3 mg increments. The maximum recommended dosage is 6 mg orally once daily. In short-term controlled trials, dosages above 6 mg daily do not confer increased effectiveness sufficient to outweigh dose-related adverse reactions [see Adverse Reactions (6.1), Clinical Studies (14.2)].

Pediatric Patients (10 to 17 years of age)

The starting dosage of VRAYLAR is 0.5 mg orally once daily. The recommended dosage is 3 mg or 4.5 mg orally once daily. Increase the dosage to 1.5 mg orally once daily on Day 3 and to 3 mg orally once daily on Day 5. Depending upon clinical response and tolerability, the dosage may be increased to 4.5 mg orally once daily starting on Day 8. The maximum recommended dosage is 4.5 mg orally once daily.

2.4 Recommended Dosage in Depressive Episodes Associated with Bipolar I Disorder (Bipolar Depression) in Adult Patients

The starting dosage of VRAYLAR is 1.5 mg orally once daily. Depending upon clinical response and tolerability, the dosage can be increased to 3 mg orally once daily on Day 15. Maximum recommended dosage is 3 mg orally once daily.

2.5 Recommended Dosage for Adjunctive Therapy to Antidepressants for the Treatment of Major Depressive Disorder in Adult Patients

The starting dosage of VRAYLAR is 1.5 mg orally once daily. Depending upon clinical response and tolerability, the dosage can be increased to 3 mg orally once daily on Day 15. In clinical trials, dosage titration at intervals of less than 14 days resulted in a higher incidence of adverse reactions [see Adverse Reactions (6.1)]. Maximum recommended dosage is 3 mg orally once daily.

2.6 Dosage Modifications for CYP3A4 Inhibitors and Inducers

Initiating VRAYLAR While Taking a Strong or Moderate CYP3A4 Inhibitor

Dosage modifications for the starting dosage of VRAYLAR in adult patients taking a strong or moderate CYP3A4 inhibitor are presented in Table 1:

Table 1: Dosage Modifications for the Starting Dosage of VRAYLAR in Adult Patients Taking a Strong or Moderate CYP3A4 Inhibitor

Adult Patients | VRAYLAR Starting Dosage
 | When Taking a Strong CYP3A4 Inhibitor | When Taking a Moderate CYP3A4 Inhibitor
Schizophrenia | Start at 0.5 mg orally once daily; increase to 0.75 mg orally once daily, if needed* | Start at 0.75 mg orally once daily; increase to 1.5 mg orally daily, if needed*
Bipolar Mania
Bipolar Depression | 0.5 mg orally once daily | 0.75 mg orally once daily
Adjunctive therapy for treatment of MDD

*Depending upon clinical response and tolerability.

Initiating VRAYLAR is not recommended in pediatric patients while taking a strong or moderate CYP3A4 Inhibitor.

Initiating a Strong or Moderate CYP3A4 Inhibitor While Taking a Stable Dosage of VRAYLAR

Dosage recommendations for adult and pediatric patients initiating a strong or moderate CYP3A4 inhibitor while on a stable dose of VRAYLAR (see Table 2):

Table 2: Dosage Modifications for VRAYLAR When Initiating a Strong or Moderate CYP3A4 Inhibitor and While Taking a Stable Dosage of VRAYLAR in Adult and Pediatric Patients

Currently on VRAYLAR Dosage | VRAYLAR Dosage When Initiating a Strong CYP3A4 Inhibitor | VRAYLAR Dosage When Initiating a Moderate CYP3A4 Inhibitor
1.5 mg or 3 mg once daily | 0.5 mg orally once daily | 0.75 mg orally once daily
4.5 mg or 6 mg once daily | 0.75 mg orally once daily | 1.5 mg orally once daily

When the strong or moderate CYP3A4 inhibitor is discontinued, the VRAYLAR dosage may need to be increased based on clinical response and tolerability [see Drug Interactions (7)].

Dosage Modifications for Patients Concomitantly Taking VRAYLAR with CYP3A4 Inducers

Concomitant use of VRAYLAR and a CYP3A4 inducer has not been evaluated and is not recommended [see Dosage and Administration (2.1), Warnings and Precautions (5.6), Drug Interactions (7), Clinical Pharmacology (12.3)].

2.7 Treatment Discontinuation

Following discontinuation of VRAYLAR, the decline in plasma concentrations of active drug and metabolites may not be immediately reflected in patients’ clinical symptoms; the plasma concentration of cariprazine and its active metabolites will decline by 50% in ~1 week [see Clinical Pharmacology (12.3)]. There are no systematically collected data to specifically address switching patients from VRAYLAR to other antipsychotics or concerning concomitant administration with other antipsychotics.

3. DOSAGE FORMS AND STRENGTHS

VRAYLAR (cariprazine) capsules are available in six strengths.

- 0.5 mg capsules: Ivory to yellow cap and a grey to green body imprinted with “FL 0.5”
- 0.75 mg capsules: Grey to green cap and blue body imprinted with “FL 0.75”
- 1.5 mg capsules: White cap and body imprinted with “FL 1.5”
- 3 mg capsules: Green to blue-green cap and white body imprinted with “FL 3”
- 4.5 mg capsules: Green to blue-green cap and body imprinted with “FL 4.5”
- 6 mg capsules: Purple cap and white body imprinted with “FL 6”

4. CONTRAINDICATIONS

VRAYLAR is contraindicated in patients with history of a hypersensitivity reaction to cariprazine. Reactions have ranged from rash, pruritus, urticaria, and reactions suggestive of angioedema (e.g., swollen tongue, lip swelling, face edema, pharyngeal edema, and swelling face).

5. WARNINGS AND PRECAUTIONS

5.1 Increased Mortality in Elderly Patients with Dementia-Related Psychosis

Antipsychotic drugs increase the all-cause risk of death in elderly patients with dementia-related psychosis. Analyses of 17 dementia-related psychosis placebo-controlled trials (modal duration of 10 weeks and largely in patients taking atypical antipsychotic drugs) revealed a risk of death in the drug-treated patients of between 1.6 to 1.7 times that in placebo-treated patients. Over the course of a typical 10-week controlled trial, the rate of death in drug-treated patients was about 4.5%, compared to a rate of about 2.6% in placebo-treated patients.

Although the causes of death were varied, most of the deaths appeared to be either cardiovascular (e.g., heart failure, sudden death) or infectious (e.g., pneumonia) in nature. VRAYLAR is not approved for the treatment of patients with dementia-related psychosis [see Boxed Warning, Warnings and Precautions (5.3)].

5.2 Suicidal Thoughts and Behaviors in Children, Adolescents and Young Adults

In pooled analyses of placebo-controlled trials of antidepressant drugs (SSRIs and other antidepressant classes) that included approximately 77,000 adult patients and 4,500 pediatric patients, the incidence of suicidal thoughts and behaviors in antidepressant-treated patients age 24 years and younger was greater than in placebo-treated patients. There was considerable variation in risk of suicidal thoughts and behaviors among drugs, but there was an increased risk identified in young patients for most drugs studied. There were differences in absolute risk of suicidal thoughts and behaviors across the different indications, with the highest incidence in patients with MDD. The drug-placebo differences in the number of cases of suicidal thoughts and behaviors per 1000 patients treated are provided in Table 3.

Table 3: Risk Differences of the Number of Patients of Suicidal Thoughts and Behavior in the Pooled Placebo-Controlled Trials of Antidepressants in Pediatric and Adult Patients
Age Range | Drug-Placebo Difference in Number of Patients of Suicidal Thoughts or Behaviors per 1000 Patients Treated
 | Increases Compared to Placebo
<18 years old | 14 additional patients
18-24 years old | 5 additional patients
 | Decreases Compared to Placebo
25-64 years old | 1 fewer patient
≥65 years old | 6 fewer patients

It is unknown whether the risk of suicidal thoughts and behaviors in children, adolescents, and young adults extends to longer-term use, i.e., beyond four months. However, there is substantial evidence from placebo-controlled maintenance trials in adults with MDD that antidepressants delay the recurrence of depression and that depression itself is a risk factor for suicidal thoughts and behaviors.

Monitor all antidepressant-treated patients for any indication for clinical worsening and emergence of suicidal thoughts and behaviors, especially during the initial few months of drug therapy, and at times of dosage changes. Counsel family members or caregivers of patients to monitor for changes in behavior and to alert the healthcare provider. Consider changing the therapeutic regimen, including possibly discontinuing VRAYLAR, in patients whose depression is persistently worse, or who are experiencing emergent suicidal thoughts or behaviors.

5.3 Cerebrovascular Adverse Reactions, Including Stroke, in Elderly Patients with Dementia-Related Psychosis

In placebo-controlled trials in elderly patients with dementia, patients randomized to risperidone, aripiprazole, and olanzapine had a higher incidence of stroke and transient ischemic attack, including fatal stroke. VRAYLAR is not approved for the treatment of patients with dementia-related psychosis [see Boxed Warning, Warnings and Precautions (5.1)].

5.4 Neuroleptic Malignant Syndrome (NMS)

Neuroleptic Malignant Syndrome (NMS), a potentially fatal symptom complex, has been reported in association with administration of antipsychotic drugs. Clinical manifestations of NMS are hyperpyrexia, muscle rigidity, delirium, and autonomic instability. Additional signs may include elevated creatine phosphokinase, myoglobinuria (rhabdomyolysis), and acute renal failure.

If NMS is suspected, immediately discontinue VRAYLAR and provide intensive symptomatic treatment and monitoring.

5.5 Tardive Dyskinesia

Tardive dyskinesia, a syndrome consisting of potentially irreversible, involuntary, dyskinetic movements, may develop in patients treated with antipsychotic drugs, including VRAYLAR. The risk appears to be highest among the elderly, especially elderly women, but it is not possible to predict which patients are likely to develop the syndrome. Whether antipsychotic drug products differ in their potential to cause tardive dyskinesia is unknown.

The risk of tardive dyskinesia and the likelihood that it will become irreversible increase with the duration of treatment and the cumulative dose. The syndrome can develop after a relatively brief treatment period, even at low doses. It may also occur after discontinuation of treatment.

Tardive dyskinesia may remit, partially or completely, if antipsychotic treatment is discontinued. Antipsychotic treatment itself, however, may suppress (or partially suppress) the signs and symptoms of the syndrome, possibly masking the underlying process. The effect that symptomatic suppression has upon the long-term course of tardive dyskinesia is unknown.

Given these considerations, VRAYLAR should be prescribed in a manner most likely to reduce the risk of tardive dyskinesia. Chronic antipsychotic treatment should generally be reserved for patients: 1) who suffer from a chronic illness that is known to respond to antipsychotic drugs; and 2) for whom alternative, effective, but potentially less harmful treatments are not available or appropriate. In patients who do require chronic treatment, use the lowest dose and the shortest duration of treatment producing a satisfactory clinical response should be sought. Periodically reassess the need for continued treatment.

If signs and symptoms of tardive dyskinesia appear in a patient on VRAYLAR, drug discontinuation should be considered. However, some patients may require treatment with VRAYLAR despite the presence of the syndrome.

5.6 Late-Occurring Adverse Reactions

Adverse reactions may first appear several weeks after the initiation of VRAYLAR treatment, probably because plasma levels of cariprazine and its major metabolites accumulate over time. As a result, the incidence of adverse reactions in short-term trials may not reflect the rates after longer term exposures [see Dosage and Administration (2.1), Adverse Reactions (6.1), Clinical Pharmacology (12.3)].

Monitor for adverse reactions, including extrapyramidal symptoms (EPS) or akathisia, and patient response for several weeks after a patient has begun VRAYLAR and after each dosage increase. Consider reducing the dose or discontinuing the drug.

5.7 Metabolic Changes

Atypical antipsychotic drugs, including VRAYLAR, have caused metabolic changes, including hyperglycemia, diabetes mellitus, dyslipidemia, and weight gain. There have been reports of hyperglycemia in patients treated with VRAYLAR. Although all drugs in the class to date have been shown to produce some metabolic changes, each drug has its own specific risk profile.

Hyperglycemia and Diabetes Mellitus

Hyperglycemia, in some cases extreme and associated with ketoacidosis or hyperosmolar coma or death, has been reported in patients treated with atypical antipsychotics. Assess fasting plasma glucose before or soon after initiation of antipsychotic medication and monitor periodically during long-term treatment.

Adult Patients with Schizophrenia

In the 6-week, placebo-controlled trials of adult patients with schizophrenia, the proportion of patients with shifts in fasting glucose from normal (<100 mg/dL) to high (≥126 mg/dL) and borderline (≥100 and <126 mg/dL) to high were similar in patients treated with VRAYLAR and placebo. In the long-term, open-label schizophrenia studies, 4% of patients with normal hemoglobin A1c baseline values developed elevated levels (≥ 6.5%).

Pediatric Patients with Schizophrenia (13 to 17 years of age)

In a long term, open-label study in pediatric patients, no patients with schizophrenia with normal (<100 mg/dL) baseline fasting serum glucose experienced a shift to high (≥126 mg/dL) while taking VRAYLAR.

Adult Patients with Bipolar Disorder

In six placebo-controlled trials up to 8-weeks of adult patients with bipolar disorder (mania or depression), the proportion of patients with shifts in fasting glucose from normal (<100 mg/dL) to high (≥126 mg/dL) and borderline (≥100 and <126 mg/dL) to high were similar in patients treated with VRAYLAR and placebo. In the long-term, open-label bipolar disorder studies, 4% patients with normal hemoglobin A1c baseline values developed elevated levels (≥ 6.5%).

Pediatric Patients with Bipolar I Mania/Mixed Episodes (10 to 17 years of age)

In a long term, open-label study in pediatric patients, 4.6% (4/87) of patients with bipolar disorder with normal (<100 mg/dL) baseline fasting serum glucose experienced a shift to high (≥126 mg/dL) while taking VRAYLAR.

Adjunctive Treatment of Major Depressive Disorder in Adult Patients

In two 6-week placebo-controlled trials of adult patients with major depressive disorder, the proportion of patients with shifts in fasting glucose from normal (<100 mg/dL) to high (≥126 mg/dL) was greatest in the VRAYLAR 3 mg per day + antidepressant therapy arm (3.2%) compared with those taking VRAYLAR 1.5 mg per day + antidepressant therapy (2%) or those placebo-treated (1.3%). The proportion of patients with shifts from normal to borderline (≥100 and <126 mg/dL) or from borderline to high were similar in patients treated with VRAYLAR and placebo. In a long-term, open-label adjunctive treatment of MDD study, 7% patients with normal hemoglobin A1c baseline values developed elevated levels (> 6%).

In one 8-week placebo-controlled trial of adult patients with major depressive disorder, the changes from baseline to end of the trial in fasting glucose were similar among the VRAYLAR and placebo + antidepressant therapy treatment groups. During the 8-week trial, serum insulin levels increased by 12 pmol/L in the VRAYLAR 1 mg to 2 mg per day group, 20 pmol/L in the VRAYLAR 2 mg to 4.5 mg per day group, and 8.5 pmol/L in the placebo group.

Dyslipidemia

Atypical antipsychotics cause adverse alterations in lipids. Before or soon after initiation of antipsychotic medication, obtain a fasting lipid profile at baseline and monitor periodically during treatment.

Adult Patients with Schizophrenia

In the 6-week, placebo-controlled trials of adult patients with schizophrenia, the proportion of patients with shifts in fasting total cholesterol, LDL, HDL, and triglycerides were similar in patients treated with VRAYLAR and placebo.

Pediatric Patients with Schizophrenia (13 to 17 years of age)

In a long term, open-label study in pediatric patients, no patients with schizophrenia experienced shifts in normal (<170 mg/dL) baseline total cholesterol to high (≥200 mg/dL), and 9.1% (1/11) of patients taking VRAYLAR experienced shifts from normal baseline HDL cholesterol (>45 mg/dL) to low (<40 mg/dL). Of patients with normal baseline fasting triglycerides, 25% (2/8) experienced shifts from normal to high (<90 to ≥ 130 mg/dL).

Adult Patients with Bipolar Disorder

In six placebo-controlled trials up to 8-weeks of adult patients with bipolar disorder (mania or depression), the proportion of patients with shifts in fasting total cholesterol, LDL, HDL, and triglycerides were similar in patients treated with VRAYLAR and placebo.

Pediatric Patients with Bipolar I Mania/Mixed Episodes (10 to 17 years of age)

In a long term, open-label study in pediatric patients, 1.2% (1/81) of patients with bipolar disorder experienced shifts in normal (<170 mg/dL) baseline total cholesterol to high (≥200 mg/dL), and 10.6% (10/94) of patients taking VRAYLAR experienced shifts from normal baseline HDL cholesterol (>45 mg/dL) to low (<40 mg/dL). Of patients with normal fasting baseline triglycerides, 20% (12/60) experienced shifts from normal to high (<90 to ≥130 mg/dL).

Adjunctive Treatment of Major Depressive Disorder in Adult Patients

In two 6-week placebo-controlled trials of adult patients with major depressive disorder, the proportion of patients with shifts in total cholesterol, fasting LDL, HDL, and fasting triglycerides were similar in patients treated with VRAYLAR and placebo.

Weight Gain

Weight gain has been observed with use of atypical antipsychotics, including VRAYLAR. Monitor weight at baseline and frequently thereafter. Tables 4, 5, 6, and 7 show the change in body weight occurring from baseline to endpoint in 6-week trials of schizophrenia, 3-week bipolar mania trials, 6-week and 8-week bipolar depression trials, and 6-week and 8-week trials of adjunctive treatment for major depressive disorder, respectively.

Adult Patients with Schizophrenia

Table 4. Change in Body Weight (kg) in 6-Week Schizophrenia Trials (Adult Patients)
 |  | VRAYLAR*
 | Placebo (N=573) | 1.5 - 3 mg/day (N=512) | 4.5 - 6 mg/day (N=570) | 9 - 12⸰ mg/day (N=203)
Mean Change at Endpoint | +0.3 | +0.8 | +1 | +1
Proportion of Patients with Weight Increase (≥7%) | 5% | 8% | 8% | 17%

*Data shown by modal daily dose, defined as most frequently administered dose per patient
⸰The maximum recommended daily dose is 6 mg. Doses above 6 mg daily do not confer increased effectiveness sufficient to outweigh dose-related adverse reactions.

In long-term, uncontrolled trials with VRAYLAR in schizophrenia, the mean changes from baseline in weight at 12, 24, and 48 weeks were 1.2 kg, 1.7 kg, and 2.5 kg, respectively.

Pediatric Patients with Schizophrenia (13 to 17 years of age)

In a long term, open-label study in pediatric patients, no subjects with schizophrenia discontinued due to weight increase. The mean change in weight from baseline to last available visit was 2.4 kg. To adjust for normal growth, z-scores were derived (measured in standard deviations [SD]), which normalize for natural growth of children and adolescents by comparisons to age- and gender-matched population standards. A z-score change <0.5 SD is considered not clinically significant. In this study, the mean change in z-score from baseline to last available visit was 0.1 SD for body weight, and no subjects had a change in z-score ≥ 0.5 SD.

Adult Patients with Bipolar Disorder

Table 5. Change in Body Weight (kg) in 3-Week Bipolar Mania Trials (Adult Patients)
 |  | VRAYLAR*
 | Placebo (N=439) | 3 - 6 mg/day (N=259) | 9 - 12⸰ mg/day (N=360)
Mean Change at Endpoint | +0.2 | +0.5 | +0.6
Proportion of Patients with Weight Increase (≥7%) | 2% | 1% | 3%

*Data shown by modal daily dose, defined as most frequently administered dose per patient
⸰The maximum recommended daily dose is 6 mg. Doses above 6 mg daily do not confer increased effectiveness sufficient to outweigh dose-related adverse reactions.

Pediatric Patients with Bipolar I Mania/Mixed Episodes (10 to 17 years of age)

In a long term, open-label study in pediatric patients, no subjects with bipolar I disorder discontinued due to weight increase. The mean change in weight from baseline to last available visit was 3.1 kg. To adjust for normal growth, z-scores were derived (measured in standard deviations [SD]), which normalize for natural growth of children and adolescents by comparisons to age- and gender-matched population standards. A z-score change <0.5 SD is considered not clinically significant. In this study, the mean change in z-score from baseline to last available visit was 0.2 SD for body weight, and 14.6% of subjects had an increase in age- and sex-adjusted body weight z-score of at least 0.5 SD from baseline.

Table 6. Change in Body Weight (kg) in two 6-Week and one 8-Week Bipolar Depression Trials (Adult Patients)
 |  | VRAYLAR
 | Placebo | 1.5 mg/day | 3 mg/day
 | (N=463) | (N=467) | (N=465)
Mean Change at Endpoint | -0.1 | +0.7 | +0.4
Proportion of Patients with Weight Increase (≥7%) | 1% | 3% | 3%

Adjunctive Treatment of Major Depressive Disorder in Adult Patients

Table 7. Change in Body Weight (kg) in two 6-Week and one 8-Week Adjunctive Treatment for Major Depressive Disorder Trials (Adult Patients)
 |  | VRAYLAR
6-Week Trials | Placebo +ADT | 1.5 mg/day +ADT | 3 mg/day +ADT
 | (N=503) | (N=502) | (N=503)
Mean Change at Endpoint | +0.2 | +0.7 | +0.7
Proportion of Patients with Weight Increase (≥7%) | 1% | 2% | 2%
8-Week Trial | Placebo + ADT (N=266) | 1 to 2 mg/day + ADT (N=273) | 2 to 4.5 mg/day + ADT (N=273)
Mean Change at Endpoint | 0 | +0.9 | +0.9
Proportion of Patients with Weight Increase (≥7%) | 2% | 2% | 3%

In the long-term, open-label adjunctive treatment of MDD trial, 2 patients (0.6%) discontinued due to weight increase. VRAYLAR was associated with mean change from baseline in weight of 1.7 kg at Week 26. In the long-term, open-label adjunctive treatment of MDD trial, 19% of patients demonstrated a ≥7% increase in body weight, and 5% demonstrated a ≥7% decrease in body weight.

5.8 Leukopenia, Neutropenia, and Agranulocytosis

Leukopenia and neutropenia have been reported during treatment with antipsychotic agents, including VRAYLAR. Agranulocytosis (including fatal cases) has been reported with other agents in the class.

Possible risk factors for leukopenia and neutropenia include pre-existing low white blood cell count (WBC) or absolute neutrophil count (ANC) and history of drug-induced leukopenia or neutropenia. In patients with a pre-existing low WBC or ANC or a history of drug-induced leukopenia or neutropenia, perform a complete blood count (CBC) frequently during the first few months of therapy. In such patients, consider discontinuation of VRAYLAR at the first sign of a clinically significant decline in WBC in the absence of other causative factors.

Monitor patients with clinically significant neutropenia for fever or other symptoms or signs of infection and treat promptly if such symptoms or signs occur. Discontinue VRAYLAR in patients with absolute neutrophil count < 1000/mm^3 and follow their WBC until recovery.

5.9 Orthostatic Hypotension and Syncope

Atypical antipsychotics cause orthostatic hypotension and syncope. Generally, the risk is greatest during initial dose titration and when increasing the dose. Symptomatic orthostatic hypotension was infrequent in trials of VRAYLAR and was not more frequent on VRAYLAR than placebo. Syncope was not observed.

Orthostatic vital signs should be monitored in patients who are vulnerable to hypotension (e.g., elderly patients, patients with dehydration, hypovolemia, and concomitant treatment with antihypertensive medications), patients with known cardiovascular disease (history of myocardial infarction, ischemic heart disease, heart failure, or conduction abnormalities), and patients with cerebrovascular disease. VRAYLAR has not been evaluated in patients with a recent history of myocardial infarction or unstable cardiovascular disease. Such patients were excluded from pre-marketing clinical trials.

5.10 Falls

Antipsychotics, including VRAYLAR, may cause somnolence, postural hypotension, motor and sensory instability, which may lead to falls and, consequently, fractures or other injuries. For patients with diseases, conditions, or medications that could exacerbate these effects, complete fall risk assessments when initiating antipsychotic treatment and recurrently for patients on long-term antipsychotic therapy.

5.11 Seizures

Like other antipsychotic drugs, VRAYLAR may cause seizures. This risk is greatest in patients with a history of seizures or with conditions that lower the seizure threshold. Conditions that lower the seizure threshold may be more prevalent in older patients.

5.12 Potential for Cognitive and Motor Impairment

VRAYLAR, like other antipsychotics, may cause somnolence and has the potential to impair judgment, thinking, or motor skills.

In 6-week schizophrenia trials, somnolence (hypersomnia, sedation, and somnolence) was reported in 7% of VRAYLAR-treated patients compared to 6% of placebo-treated patients. In 3-week bipolar mania trials, somnolence was reported in 8% of VRAYLAR-treated patients compared to 4% of placebo-treated patients. In two 6-week and one 8-week trials of depressive episodes of bipolar I disorder, VRAYLAR-treated patients reported 7% somnolence and 4% in the placebo-treated patients. In 6-week adjunctive treatment of major depressive disorder trials, somnolence was reported in 6% of VRAYLAR-treated patients compared to 4% of placebo-treated patients. In one 8-week adjunctive treatment of major depressive disorder trial, somnolence was reported in 11% of VRAYLAR-treated patients compared to 6% of placebo-treated patients.

Patients should be cautioned about operating hazardous machinery, including motor vehicles, until they are reasonably certain that therapy with VRAYLAR does not affect them adversely.

5.13 Body Temperature Dysregulation

Atypical antipsychotics may disrupt the body’s ability to reduce core body temperature. Strenuous exercise, exposure to extreme heat, dehydration, and anticholinergic medications may contribute to an elevation in core body temperature; use VRAYLAR with caution in patient who may experience these conditions.

5.14 Dysphagia

Esophageal dysmotility and aspiration have been associated with antipsychotic drug use. Dysphagia has been reported with VRAYLAR. VRAYLAR and other antipsychotic drugs should be used cautiously in patients at risk for aspiration.

6 ADVERSE REACTIONS

The following adverse reactions are discussed in more detail in other sections of the labeling:

- Increased Mortality in Elderly Patients with Dementia-Related Psychosis [see Boxed Warning and Warnings and Precautions (5.1)]
- Suicidal Thoughts and Behaviors [see Boxed Warning and Warnings and Precautions (5.2)]
- Cerebrovascular Adverse Reactions, Including Stroke, in Elderly Patients with Dementia-Related Psychosis [see Warnings and Precautions (5.3)]
- Neuroleptic Malignant Syndrome [see Warnings and Precautions (5.4)]
- Tardive Dyskinesia [see Warnings and Precautions (5.5)]
- Late Occurring Adverse Reactions [see Warnings and Precautions (5.6)]
- Metabolic Changes [see Warnings and Precautions (5.7)]
- Leukopenia, Neutropenia, and Agranulocytosis [see Warnings and Precautions (5.8)]
- Orthostatic Hypotension and Syncope [see Warnings and Precautions (5.9)]
- Falls [see Warnings and Precautions (5.10)]
- Seizures [see Warnings and Precautions (5.11)]
- Potential for Cognitive and Motor Impairment [see Warnings and Precautions (5.12)]
- Body Temperature Dysregulation [see Warnings and Precautions (5.13)]
- Dysphagia [see Warnings and Precautions (5.14)]

6.1 Clinical Trials Experience

Because clinical trials are conducted under widely varying conditions, adverse reaction rates observed in the clinical trials of a drug cannot be directly compared to rates in the clinical trials of another drug and may not reflect the rates observed in practice.

The information below is derived from an integrated clinical study database for VRAYLAR consisting of 6,722 adult patients exposed to one or more doses of VRAYLAR for the treatment of schizophrenia, manic or mixed episodes associated with bipolar I disorder, bipolar depression, and adjunctive treatment of major depressive disorder in placebo-controlled studies. This experience corresponds with a total experience of 1,182.8 patient-years. A total of 4,329 VRAYLAR-treated patients had at least 6 weeks and 296 VRAYLAR-treated patients had at least 48 weeks of exposure.

Adult Patients with Schizophrenia

The following findings are based on four placebo-controlled, 6-week schizophrenia trials with VRAYLAR doses ranging from 1.5 to 12 mg once daily. The maximum recommended dosage is 6 mg daily.

Adverse Reactions Associated with Discontinuation of Treatment: There was no single adverse reaction leading to discontinuation that occurred at a rate of ≥ 2% in VRAYLAR-treated patients and at least twice the rate of placebo.

Common Adverse Reactions (≥ 5% and at least twice the rate of placebo): extrapyramidal symptoms and akathisia.

Adverse Reactions with an incidence of ≥ 2% and greater than placebo, at any dose are shown in Table 8.

Table 8. Adverse Reactions Occurring in ≥ 2% of VRAYLAR-treated Patients and > Placebo-treated Adult Patients in 6-Week Schizophrenia Trials
 |  | VRAYLAR*
System Organ Class / Preferred Term | Placebo (N= 584) (%) | 1.5 to 3 mg/day (N=539) (%) | 4.5 to 6 mg/day (N=575) (%) | 9 to 12 mg/day⸰ (N=203) (%)
Cardiac Disorders
Tachycardiaa | 1 | 2 | 2 | 3
Gastrointestinal Disorders
Abdominal painb | 5 | 3 | 4 | 7
Constipation | 5 | 6 | 7 | 10
Diarrheac | 3 | 1 | 4 | 5
Dry Mouth | 2 | 1 | 2 | 3
Dyspepsia | 4 | 4 | 5 | 5
Nausea | 5 | 5 | 7 | 8
Toothache | 4 | 3 | 3 | 6
Vomiting | 3 | 4 | 5 | 5
General Disorders/Administration Site Conditions
Fatigued | 1 | 1 | 3 | 2
Infections and Infestations
Nasopharyngitis | 1 | 1 | 1 | 2
Urinary tract infection | 1 | 1 | <1 | 2
Investigations
Blood creatine phosphokinase increased | 1 | 1 | 2 | 3
Hepatic enzyme increasede | <1 | 1 | 1 | 2
Weight increased | 1 | 3 | 2 | 3
Metabolism and Nutrition Disorders
Decreased appetite | 2 | 1 | 3 | 2
Musculoskeletal and Connective Tissue Disorders
Arthralgia | 1 | 2 | 1 | 2
Back pain | 2 | 3 | 3 | 1
Pain in extremity | 3 | 2 | 2 | 4
Nervous System Disorders
Akathisia | 4 | 9 | 13 | 14
Extrapyramidal symptomsf | 8 | 15 | 19 | 20
Headacheg | 13 | 9 | 11 | 18
Somnolenceh | 5 | 5 | 8 | 10
Dizziness | 2 | 3 | 5 | 5
Psychiatric Disorders
Agitation | 4 | 3 | 5 | 3
Insomniai | 11 | 12 | 13 | 11
Restlessness | 3 | 4 | 6 | 5
Anxiety | 4 | 6 | 5 | 3
Respiratory, Thoracic and Mediastinal Disorders
Cough | 2 | 1 | 2 | 4
Skin and Subcutaneous Disorders
Rash | 1 | <1 | 1 | 2
Vascular Disorders
Hypertensionj | 1 | 2 | 3 | 6

Note: Figures rounded to the nearest integer
* Data shown by modal daily dose, defined as most frequently administered dose per patient
a Tachycardia terms: heart rate increased, sinus tachycardia, tachycardia
b Abdominal pain terms: abdominal discomfort, abdominal pain, abdominal pain lower, abdominal pain upper, gastrointestinal pain
c Diarrhea terms: diarrhea, frequent bowel movements
d Fatigue terms: asthenia, fatigue
e Hepatic enzyme increase terms: alanine aminotransferase increased, aspartate aminotransferase increased, hepatic enzyme increased
f Extrapyramidal Symptoms terms: bradykinesia, cogwheel rigidity, drooling, dyskinesia, dystonia, extrapyramidal disorder, hypokinesia, masked facies, muscle rigidity, muscle tightness, musculoskeletal stiffness, oculogyric crisis, oromandibular dystonia, parkinsonism, salivary hypersecretion, tardive dyskinesia, torticollis, tremor, trismus
g Headache terms: headache, tension headache
h Somnolence terms: hypersomnia, sedation, somnolence
i Insomnia terms: initial insomnia, insomnia, middle insomnia, terminal insomnia
j Hypertension terms: blood pressure diastolic increased, blood pressure increased, blood pressure systolic increased, hypertension
⸰The maximum recommended daily dose is 6 mg. Doses above 6 mg daily do not confer increased effectiveness sufficient to outweigh dose-related adverse reactions.

Adult Patients with Bipolar Mania

The following findings are based on three placebo-controlled, 3-week bipolar mania trials with VRAYLAR doses ranging from 3 to 12 mg once daily. The maximum recommended dosage is 6 mg daily.

Adverse Reactions Associated with Discontinuation of Treatment: The adverse reaction leading to discontinuation that occurred at a rate of ≥ 2% in VRAYLAR-treated patients and at least twice the rate of placebo was akathisia (2%). Overall, 12% of the patients who received VRAYLAR discontinued treatment due to an adverse reaction, compared with 7% of placebo-treated patients in these trials.

Common Adverse Reactions (≥ 5% and at least twice the rate of placebo): extrapyramidal symptoms, akathisia, dyspepsia, vomiting, somnolence, and restlessness.

Adverse Reactions with an incidence of ≥ 2% and greater than placebo at any dose are shown in Table 9.

Table 9. Adverse Reactions Occurring in ≥ 2% of VRAYLAR-treated Patients and > Placebo-treated Adult Patients in 3-Week Bipolar Mania Trials
 |  | VRAYLAR*
System Organ Class / Preferred Term | Placebo (N= 442) (%) | 3 to 6 mg/day (N=263) (%) | 9 to 12 mg/day⸰ (N=360) (%)
Cardiac Disorders
Tachycardiaa | 1 | 2 | 1
Eye Disorders
Vision blurred | 1 | 4 | 4
Gastrointestinal Disorders
Nausea | 7 | 13 | 11
Constipation | 5 | 6 | 11
Vomiting | 4 | 10 | 8
Dry mouth | 2 | 3 | 2
Dyspepsia | 4 | 7 | 9
Abdominal painb | 5 | 6 | 8
Diarrheac | 5 | 5 | 6
Toothache | 2 | 4 | 3
General Disorders/Administration Site Conditions
Fatigued | 2 | 4 | 5
Pyrexiae | 2 | 1 | 4
Investigations
Blood creatine phosphokinase increased | 2 | 2 | 3
Hepatic enzymes increasedf | <1 | 1 | 3
Weight increased | 2 | 2 | 3
Metabolism and Nutrition Disorders
Decreased appetite | 3 | 3 | 4
Musculoskeletal and Connective Tissue Disorders
Pain in extremity | 2 | 4 | 2
Back pain | 1 | 1 | 3
Nervous System Disorders
Akathisia | 5 | 20 | 21
Extrapyramidal Symptomsg | 12 | 26 | 29
Headacheh | 13 | 14 | 13
Dizziness | 4 | 7 | 6
Somnolencei | 4 | 7 | 8
Psychiatric Disorders
Insomniaj | 7 | 9 | 8
Restlessness | 2 | 7 | 7
Respiratory, thoracic and mediastinal disorders
Oropharyngeal pain | 2 | 1 | 3
Vascular Disorders
Hypertensionk | 1 | 5 | 4

Note: Figures rounded to the nearest integer
*Data shown by modal daily dose, defined as most frequently administered dose per patient
a Tachycardia terms: heart rate increased, sinus tachycardia, tachycardia
b Abdominal pain terms: abdominal discomfort, abdominal pain, abdominal pain upper, abdominal tenderness
c Diarrhea: diarrhea, frequent bowel movements
d Fatigue terms: asthenia, fatigue
e Pyrexia terms: body temperature increased, pyrexia
f Hepatic enzymes increased terms: alanine aminotransferase increased, aspartate aminotransferase increased, hepatic enzyme increased, transaminases increased
g Extrapyramidal Symptoms terms: bradykinesia, drooling, dyskinesia, dystonia, extrapyramidal disorder, hypokinesia, muscle rigidity, muscle tightness, musculoskeletal stiffness, oromandibular dystonia, parkinsonism, salivary hypersecretion, tremor
h Headache terms: headache, tension headache
i Somnolence terms: hypersomnia, sedation, somnolence
j Insomnia terms: initial insomnia, insomnia, middle insomnia
k Hypertension terms: blood pressure diastolic increased, blood pressure increased, hypertension
⸰ The maximum recommended daily dose is 6 mg. Doses above 6 mg daily do not confer increased effectiveness sufficient to outweigh dose-related adverse reactions.

Adult Patients with Bipolar Depression

The following findings are based on three placebo-controlled, two 6-week and one 8-week bipolar depression trials with VRAYLAR doses of 1.5 mg and 3 mg once daily.

Adverse Reactions Associated with Discontinuation of Treatment: There were no adverse reaction leading to discontinuation that occurred at a rate of ≥ 2% in VRAYLAR-treated patients and at least twice the rate of placebo. Overall, 6% of the patients who received VRAYLAR discontinued treatment due to an adverse reaction, compared with 5% of placebo-treated patients in these trials.

Common Adverse Reactions (≥ 5% and at least twice the rate of placebo): nausea, akathisia, restlessness, and extrapyramidal symptoms.

Adverse Reactions with an incidence of ≥ 2% and greater than placebo at 1.5 mg or 3 mg doses are shown in Table 10.

Table 10. Adverse Reactions Occurring in ≥ 2% of VRAYLAR-treated Patients and > Placebo-treated Adult Patients in Two 6-Week and One 8-Week Bipolar Depression Trials
 |  | VRAYLAR
 | Placebo (N=468) (%) | 1.5 mg/day (N=470) (%) | 3 mg/day (N=469) (%)
Restlessness | 3 | 2 | 7
Akathisia | 2 | 6 | 10
Extrapyramidal symptomsa | 2 | 4 | 6
Dizziness | 2 | 4 | 3
Somnolenceb | 4 | 7 | 6
Nausea | 3 | 7 | 7
Increased appetite | 1 | 3 | 3
Weight increase | <1 | 2 | 2
Fatiguec | 2 | 4 | 3
Insomniad | 7 | 7 | 10

a Extrapyramidal symptoms terms: akinesia, drooling, dyskinesia, dystonia, extrapyramidal disorder, hypokinesia, muscle tightness, musculoskeletal stiffness, myoclonus, oculogyric crisis, salivary hypersecretion, tardive dyskinesia, tremor
b Somnolence terms: hypersomnia, sedation, somnolence
c Fatigue terms: asthenia, fatigue, malaise
d Insomnia terms: initial insomnia, insomnia, insomnia related to another mental condition, middle insomnia, sleep disorder, terminal insomnia

Adjunctive Therapy in Major Depressive Disorder in Adult Patients

The following findings are based on two placebo-controlled, fixed-dose 6-week trials with VRAYLAR doses of 1.5 and 3 mg once daily plus an antidepressant and one placebo-controlled, flexible-dose 8-week trial with VRAYLAR doses of (1 to 2 mg) and (2 to 4.5 mg) once daily plus an antidepressant for adjunctive therapy in MDD.

Adverse Reactions Associated with Discontinuation of Treatment: The adverse reaction leading to discontinuation that occurred at a rate of ≥ 2% in VRAYLAR-treated patients and at least twice the rate of placebo was akathisia (2%). Overall, 6% of the patients who received VRAYLAR discontinued treatment due to an adverse reaction, compared with 3% of placebo-treated patients in these trials.

Common Adverse Reactions (≥ 5% and at least twice the rate of placebo): Akathisia, nausea, and insomnia occurred in two 6-week, fixed-dose trials. Akathisia, restlessness, fatigue, constipation, nausea, increased appetite, dizziness, insomnia, and extrapyramidal symptoms occurred in one 8-week flexible-dose trial.

Adverse Reactions with an incidence of ≥ 2% and greater than placebo at 1.5 mg or 3 mg doses are shown in Table 11.

Table 11. Adverse Reactions Occurring in ≥ 2% of VRAYLAR-Treated Patients and > Placebo-Treated Adult Patients in Two Fixed-Dose 6-Week Placebo-Controlled Trials of Adjunctive Treatment of Major Depressive Disorder
System Organ Class/ Preferred Term | Placebo + ADT (N=503) (%) | VRAYLAR
 |  | 1.5 mg/day + ADT (N=502) (%) | 3 mg/day + ADT (N=503) (%)
Eye Disorders
Vision Blurred | <1 | <1 | 2
Gastrointestinal Disorders
Nausea | 3 | 7 | 6
Dry Mouth | 2 | 3 | 3
Constipation | 1 | 2 | 2
Vomiting | 1 | 1 | 2
General Disorders
Fatigue | 2 | 3 | 3
Investigations
Weight increased | 1 | 2 | 2
Nervous System Disorders
Akathisiaa | 2 | 7 | 10
Somnolenceb | 4 | 5 | 7
Extrapyramidal Symptomsc | 4 | 5 | 6
Psychiatric Disorders
Insomniad | 5 | 9 | 10
Restlessness | 2 | 4 | 4
Anxiety | 1 | 2 | 1
Skin and Subcutaneous Tissue Disorders
Hyperhidrosis | 1 | 1 | 2

Note: Figures rounded to the nearest integer
a Akathisia terms: akathisia, psychomotor hyperactivity, feeling jittery, nervousness, tension
b Somnolence terms: hypersomnia, sedation, lethargy, somnolence
c Extrapyramidal symptoms terms: drooling, dyskinesia, extrapyramidal disorder, hypotonia, muscle contractions involuntary, muscle rigidity, muscle spasms, muscle tightness, muscle twitching, musculoskeletal stiffness, myoclonus, oromandibular dystonia, parkinsonism, resting tremor, restless legs syndrome, stiff leg syndrome, salivary hypersecretion, stiff tongue, tardive dyskinesia, tremor, trismus
d Insomnia terms: initial insomnia, insomnia, middle insomnia, poor sleep quality, sleep disorder, terminal insomnia

Adverse Reactions with an incidence of ≥ 2% and greater than placebo at 1 mg to 2 mg per day or 2 mg to 4.5 mg per day doses are shown in Table 12.

Table 12. Adverse Reactions Occurring in ≥ 2% of VRAYLAR-Treated Patients and > Placebo-Treated Adult Patients in a Flexible-dose 8-Week Placebo-Controlled Trial of Adjunctive Treatment of Major Depressive Disorder
System Organ Class/ Preferred Term | Placebo + ADT (N=266) (%) | VRAYLAR 1 to 2 mg/day + ADT (N=273) (%) | VRAYLAR 2 to 4.5 mg/day + ADT (N=273) (%)
Cardiac disorders
Palpitations | 1 | 2 | <1
Eye disorders
Vision blurred | 1 | 1 | 4
Gastrointestinal disorders
Nausea | 5 | 7 | 13
Constipation | 2 | 2 | 5
Dry mouth | 3 | 5 | 4
Vomiting | <1 | 1 | 3
General disorders
Fatigue | 4 | 7 | 10
Edema | <1 | 2 | 1
Infections
Nasopharyngitis | 2 | 4 | 1
Investigations
Increased appetite | 2 | 2 | 5
Weight increased | 1 | 2 | 3
Musculoskeletal and Connective Tissue disorders
Back pain | 1 | 2 | 3
Myalgia | 0 | 1 | 2
Nervous System disorders
Akathisiaa | 3 | 8 | 23
Extrapyramidal symptomsb | 5 | 12 | 18
Somnolencec | 6 | 10 | 11
Dizziness | 2 | 4 | 5
Psychiatric disorders
Insomniad | 8 | 14 | 16
Restlessness | 3 | 8 | 8
Agitation | <1 | <1 | 3
Anxiety | <1 | 1 | 3

a Akathisia terms: akathisia, feeling jittery, nervousness, tension
b Extrapyramidal symptoms terms: cogwheel rigidity, drooling, dyskinesia, extrapyramidal disorder, hypertonia, jaw stiffness, muscle contractions involuntary, muscle disorder, muscle rigidity, muscle spasms, muscle tightness, muscle twitching, musculoskeletal stiffness, nuchal rigidity, parkinsonism, psychomotor retardation, reduced facial expression, resting tremor, restless legs syndrome, sensation of heaviness, salivary hypersecretion, tremor
c Somnolence terms: hypersomnia, sedation, lethargy, somnolence
d Insomnia terms: initial insomnia, insomnia, middle insomnia, terminal insomnia, sleep disorder, poor sleep quality

Dystonia

Symptoms of dystonia, prolonged abnormal contractions of muscle groups, may occur in susceptible individuals during the first few days of treatment. Dystonic symptoms include: spasm of the neck muscles, sometimes progressing to tightness of the throat, swallowing difficulty, difficulty breathing, and/or protrusion of the tongue. Although these symptoms can occur at low doses, they occur more frequently and with greater severity with high potency and higher doses of first-generation antipsychotic drugs. An elevated risk of acute dystonia is observed in males and younger age groups.

Extrapyramidal Symptoms (EPS) and Akathisia

In schizophrenia, bipolar mania, bipolar depression and adjunctive treatment of major depressive disorder trials, data were objectively collected using the Simpson Angus Scale (SAS) for treatment-emergent EPS (parkinsonism) (SAS total score ≤ 3 at baseline and > 3 post-baseline) and the Barnes Akathisia Rating Scale (BARS) for treatment-emergent akathisia (BARS total score ≤ 2 at baseline and > 2 post-baseline).

In 6-week schizophrenia trials, the incidence of reported adverse reactions related to extrapyramidal symptoms (EPS), excluding akathisia and restlessness was 17% for VRAYLAR-treated patients versus 8% for placebo-treated patients. These reactions led to discontinuation in 0.3% of VRAYLAR-treated patients versus 0.2% of placebo-treated patients. The incidence of akathisia was 11% for VRAYLAR-treated patients versus 4% for placebo-treated patients. These reactions led to discontinuation in 0.5% of VRAYLAR-treated patients versus 0.2% of placebo-treated patients.

In 3-week bipolar mania trials, the incidence of reported adverse reactions related to extrapyramidal symptoms (EPS), excluding akathisia and restlessness, was 28% for VRAYLAR-treated patients versus 12% for placebo-treated patients. These reactions led to a discontinuation in 1% of VRAYLAR-treated patients versus 0.2% of placebo-treated patients. The incidence of akathisia was 20% for VRAYLAR-treated patients versus 5% for placebo-treated patients. These reactions led to discontinuation in 2% of VRAYLAR-treated patients versus 0% of placebo-treated patients.

In the two 6-week and one 8-week bipolar depression trials, the incidence of reported adverse reactions related to EPS, excluding akathisia and restlessness was 4% for VRAYLAR-treated patients versus 2% for placebo-treated patients. These reactions led to discontinuation in 0.4% of VRAYLAR-treated patients versus 0% of placebo-treated patients. The incidence of akathisia was 8% for VRAYLAR-treated patients versus 2% for placebo-treated patients. These reactions led to discontinuation in 1.5% of VRAYLAR-treated patients versus 0% of placebo-treated patients.

In the two 6-week adjunctive treatment of major depressive disorder trials, the incidence of reported adverse reactions related to EPS, excluding akathisia and restlessness, was 6% for VRAYLAR-treated patients versus 4% for placebo-treated patients. These reactions led to discontinuation in 0.3% of VRAYLAR-treated patients versus 0.6% of placebo-treated patients. The combined incidence of akathisia and restlessness was 12% for VRAYLAR-treated patients versus 4% for placebo-treated patients. These reactions led to discontinuation in 2% of VRAYLAR-treated patients versus 0.4% of placebo-treated patients.

In one 8-week adjunctive treatment of major depressive disorder trial, the incidence of reported adverse reactions related to EPS, excluding akathisia and restlessness, was 12% for VRAYLAR-treated patients versus 5% for placebo-treated patients. These reactions led to discontinuation in 1% of VRAYLAR-treated patients versus 0.4% of placebo-treated patients. The incidence of akathisia and restlessness was 22% for VRAYLAR-treated patients versus 6% for placebo-treated patients. These reactions led to discontinuation in 3% of VRAYLAR-treated patients versus 0.0% of placebo-treated patients.

Cataracts

The development of cataracts was observed in nonclinical studies [see Nonclinical Toxicology (13.2)]. Cataracts were reported during the premarketing clinical trials of cariprazine; however, the duration of trials was too short to assess any association to cariprazine usage.

Vital Signs Changes

There were no clinically meaningful differences between VRAYLAR-treated patients and placebo-treated patients in mean change from baseline to endpoint in supine blood pressure parameters except for an increase in supine diastolic blood pressure in the 9 - 12 mg/day VRAYLAR-treated patients with schizophrenia.

Pooled data from 6-week schizophrenia trials are shown in Table 13, and from 3-week bipolar mania trials are shown in Table 14.

Table 13. Mean Change in Blood Pressure at Endpoint in 6-Week Schizophrenia Trials (Adult Patients)
 | Placebo (N=574) | VRAYLAR*
 |  | 1.5 - 3 mg/day (N=512) | 4.5 - 6 mg/day (N=570) | 9 - 12 mg/day⸰ (N=203)
Supine Systolic Blood Pressure (mmHg) | +0.9 | +0.6 | +1.3 | +2.1
Supine Diastolic Blood Pressure (mmHg) | +0.4 | +0.2 | +1.6 | +3.4

* Data shown by modal daily dose, defined as most frequently administered dose per patient
⸰ The maximum recommended daily dose is 6 mg. Doses above 6 mg daily do not confer increased effectiveness sufficient to outweigh dose-related adverse reactions.

Table 14. Mean Change in Blood Pressure at Endpoint in 3-Week Bipolar Mania Trials (Adult Patients)
 | Placebo (N=439) | VRAYLAR*
 |  | 3 - 6 mg/day (N=259) | 9 – 12 mg/day⸰ (N=360)
Supine Systolic Blood Pressure (mmHg) | -0.5 | +0.8 | +1.8
Supine Diastolic Blood Pressure (mmHg) | +0.9 | +1.5 | +1.9

* Data shown by modal daily dose, defined as most frequently administered dose per patient
⸰ The maximum recommended daily dose is 6 mg. Doses above 6 mg daily do not confer increased effectiveness sufficient to outweigh dose-related adverse reactions.

In the two 6-week and one 8-week bipolar depression trials, there were no clinically meaningful differences between VRAYLAR-treated patients and placebo-treated patients in mean change from baseline to endpoint in supine systolic and diastolic blood pressure. VRAYLAR-treated patients’ supine blood pressure increased by 0.1 to 0.3 mmHg; placebo-treated patients’ supine blood pressure increased by 0.2 mmHg.

In two 6-week and one 8-week adjunctive treatment of major depressive disorder trials, there were no clinically meaningful differences between VRAYLAR-treated patients and placebo-treated patients in mean change from baseline to endpoint in supine systolic and diastolic blood pressure. At the end of the 6-week trials, VRAYLAR-treated patients’ supine systolic blood pressure decreased by 0.1 to 0.7 mmHg; placebo-treated patients’ supine systolic blood pressure decreased by 0.1 mmHg. VRAYLAR-treated patients’ supine diastolic blood pressure increased by 0.1 mmHg and placebo-treated patients’ supine diastolic blood pressure increased by 0.2 mmHg.

Changes in Laboratory Tests

The proportions of patients with transaminase elevations of ≥3 times the upper limits of the normal reference range in 6-week schizophrenia trials ranged between 1% and 2% for VRAYLAR-treated patients, increasing with dose, and was 1% for placebo-treated patients. The proportions of patients with transaminase elevations of ≥3 times the upper limits of the normal reference range in 3-week bipolar mania trials ranged between 2% and 4% for VRAYLAR-treated patients depending on dose group administered and 2% for placebo-treated patients. The proportions of patients with transaminase elevations of ≥3 times the upper limits of the normal reference range in 6-week and 8-week bipolar depression trials ranged between 0% and 0.5% for VRAYLAR-treated patients depending on dose group administered and 0.4% for placebo-treated patients. The proportions of patients with transaminase elevations of ≥3 times the upper limits of the normal reference range in two 6-week adjunctive treatment of major depressive disorder trials ranged between 0% and 1% for VRAYLAR-treated patients depending on dose group administered and 0% for placebo-treated patients.

The proportions of patients with elevations of creatine phosphokinase (CPK) greater than 1000 U/L in 6-week schizophrenia trials ranged between 4% and 6% for VRAYLAR-treated patients, increasing with dose, and was 4% for placebo-treated patients. The proportions of patients with elevations of CPK greater than 1000 U/L in 3-week bipolar mania trials was about 4% in VRAYLAR and placebo-treated patients. The proportions of patients with elevations of CPK greater than 1000 U/L in 6-week and 8-week bipolar depression trials ranged between 0.2% and 1% for VRAYLAR-treated patients versus 0.2% for placebo-treated patients. The proportions of patients with elevations of CPK greater than 1000 U/L in two 6-week adjunctive treatment of major depressive disorder trials ranged between 0.6% and 0.8% for VRAYLAR-treated patients versus 0% for placebo-treated patients.

Other Adverse Reactions Observed During the Pre-marketing Evaluation of VRAYLAR

Adverse reactions listed below were reported by patients treated with VRAYLAR at doses of ≥ 1.5 mg once daily within the premarketing database of 5,763 VRAYLAR-treated patients. The reactions listed are those that could be of clinical importance, as well as reactions that are plausibly drug-related on pharmacologic or other grounds. Reactions that appear elsewhere in the VRAYLAR label are not included.

Reactions are further categorized by organ class and listed in order of decreasing frequency, according to the following definition: those occurring in at least 1/100 patients (frequent) [only those not already listed in the tabulated results from placebo-controlled studies appear in this listing]; those occurring in 1/100 to 1/1000 patients (infrequent); and those occurring in fewer than 1/1,000 patients (rare).

Gastrointestinal Disorders: Infrequent: gastroesophageal reflux disease, gastritis
Hepatobiliary Disorders: Rare: hepatitis
Metabolism and Nutrition Disorders: Frequent: decreased appetite; Rare: hyponatremia
Musculoskeletal and Connective Tissue Disorders: Rare: rhabdomyolysis
Nervous System Disorders: Rare: ischemic stroke
Psychiatric Disorders: Infrequent: suicide ideation; Rare: completed suicide, suicide attempts
Renal and Urinary Disorders: Infrequent: pollakiuria
Skin and Subcutaneous Tissue Disorders: Infrequent: hyperhidrosis

Pediatric Patients with Schizophrenia (13 to 17 years of age) or Bipolar Mania/Mixed Episodes (10 to 17 years of age)

In a long-term open-label study, safety was assessed in 164 pediatric patients with schizophrenia or bipolar I disorder, of whom 72 received VRAYLAR for at least 6 months. Adverse reactions reported in clinical studies for this age group were generally similar to those observed in adult patients.

6.2 Postmarketing Experience

The following adverse reaction has been identified during post approval use of VRAYLAR. Because these reactions are reported voluntarily from a population of uncertain size, it is not always possible to estimate their frequency or establish a causal relationship to drug exposure.

Skin and Subcutaneous Tissue Disorders – Stevens-Johnson syndrome

7 DRUG INTERACTIONS

Table 15 displays clinically significant drug interactions with VRAYLAR.

Table 15. Clinically Significant Drug Interactions with VRAYLAR
Strong or Moderate CYP3A4 Inhibitors
Clinical Impact: | Concomitant use of VRAYLAR with a strong or moderate CYP3A4 inhibitor increases the exposures of cariprazine and its major active metabolite, didesmethylcariprazine (DDCAR), compared to use of VRAYLAR alone [see Clinical Pharmacology (12.3)].
Intervention: | If VRAYLAR is used with a strong or moderate CYP3A4 inhibitor, reduce VRAYLAR dosage [see Dosage and Administration (2.6)].
CYP3A4 Inducers
Clinical Impact: | CYP3A4 is responsible for the formation and elimination of the active metabolites of cariprazine. The effect of CYP3A4 inducers on the exposure of VRAYLAR has not been evaluated, and the net effect is unclear [see Clinical Pharmacology (12.3)].
Intervention: | Concomitant use of VRAYLAR with a CYP3A4 inducer is not recommended [see Dosage and Administration (2.1, 2.6)].

8 USE IN SPECIFIC POPULATIONS

8.1 Pregnancy

Pregnancy Exposure Registry

There is a pregnancy exposure registry that monitors pregnancy outcomes in women exposed to VRAYLAR during pregnancy. For more information, contact the National Pregnancy Registry for Atypical Antipsychotics at 1-866-961-2388 or visit http://womensmentalhealth.org/clinical-and-research-programs/pregnancyregistry/.

Risk Summary

Neonates exposed to antipsychotic drugs during the third trimester of pregnancy are at risk for extrapyramidal and/or withdrawal symptoms following delivery (see Clinical Considerations). There are no available data on VRAYLAR use in pregnant women to inform any drug-associated risks for birth defects or miscarriage. The major active metabolite of cariprazine, DDCAR, has been detected in adult patients up to 12 weeks after discontinuation of VRAYLAR [see Clinical Pharmacology (12.3)].
Based on animal data, VRAYLAR may cause fetal harm.

Administration of cariprazine to rats during the period of organogenesis caused malformations, lower pup survival, and developmental delays at drug exposures less than the human exposure at the maximum recommended human dose (MRHD) of 6 mg/day. However, cariprazine was not teratogenic in rabbits at doses up to 4.6 times the MRHD of 6 mg/day [see Data].

The estimated background risk of major birth defects and miscarriage for the indicated populations is unknown. In the U.S. general population, the estimated background risk of major birth defects and miscarriage in clinically recognized pregnancies is 2-4% and 15-20%, respectively. Advise pregnant women of the potential risk to a fetus.

Clinical Considerations

Fetal/Neonatal Adverse Reactions

Extrapyramidal and/or withdrawal symptoms, including agitation, hypertonia, hypotonia, tremor, somnolence, respiratory distress, and feeding disorder have been reported in neonates whose mothers were exposed to antipsychotic drugs during the third trimester of pregnancy. These symptoms have varied in severity. Some neonates recovered within hours or days without specific treatment; others required prolonged hospitalization. Monitor neonates for extrapyramidal and/or withdrawal symptoms and manage symptoms appropriately.

Data

Animal Data

Administration of cariprazine to pregnant rats during the period of organogenesis at oral doses of 0.5, 2.5, and 7.5 mg/kg/day, which are 0.2 to 3.5 times the maximum recommended human dose (MRHD) of 6 mg/day based on AUC of total cariprazine (i.e. sum of cariprazine, DCAR, and DDCAR), caused fetal developmental toxicity at all doses, which included reduced body weight, decreased male anogenital distance, and skeletal malformations of bent limb bones, scapula, and humerus. These effects occurred in the absence or presence of maternal toxicity. Maternal toxicity, observed as a reduction in body weight and food consumption, occurred at doses 1.2 and 3.5-times the MRHD of 6 mg/day based on AUC of total cariprazine. At these doses, cariprazine caused fetal external malformations (localized fetal thoracic edema), visceral variations (undeveloped/underdeveloped renal papillae and/or distended urethrae), and skeletal developmental variations (bent ribs, unossified sternebrae). Cariprazine had no effect on fetal survival.

Administration of cariprazine to pregnant rats during pregnancy and lactation at oral doses of 0.1, 0.3, and 1 mg/kg/day, which are 0.03 to 0.4 times the MRHD of 6 mg/day based on AUC of total cariprazine, caused a decrease in postnatal survival, birth weight, and post-weaning body weight of first generation pups at the dose that is 0.4 times the MRHD of 6 mg/day based on AUC of total cariprazine in absence of maternal toxicity. First generation pups also had pale, cold bodies and developmental delays (renal papillae not developed or underdeveloped and decreased auditory startle response in males). Reproductive performance of the first generation pups was unaffected; however, the second generation pups had clinical signs and lower body weight similar to those of the first generation pups.

Administration of cariprazine to pregnant rabbits during the period of organogenesis at oral doses of 0.1, 1, and 5 mg/kg/day, which are 0.02 to 4.6 times the MRHD of 6 mg/day based on AUC of total cariprazine, was not teratogenic. Maternal body weight and food consumption were decreased at 4.6 times the MRHD of 6 mg/day based on AUC of total cariprazine; however, no adverse effects were observed on pregnancy parameters or reproductive organs.

8.2 Lactation

Risk Summary

Lactation studies have not been conducted to assess the presence of cariprazine in human milk, the effects on the breastfed infant, or the effects on milk production. Cariprazine is present in rat milk. The development and health benefits of breastfeeding should be considered along with the mother’s clinical need for VRAYLAR and any potential adverse effects on the breastfed infant from VRAYLAR or from the underlying maternal condition.

8.4 Pediatric Use

Schizophrenia

The safety and effectiveness of VRAYLAR for treatment of schizophrenia have been established in pediatric patients 13 years of age and older. Use of VRAYLAR in this population is supported by evidence from adequate and well-controlled studies in adults with schizophrenia, pharmacokinetic data from adults and pediatric patients, and safety data in pediatric patients 13 to 17 years of age [see Warnings and Precautions (5.7), Adverse Reactions (6.1), Clinical Pharmacology (12.3)]. The safety and effectiveness of VRAYLAR for the treatment of schizophrenia have not been established in pediatric patients less than 13 years of age.

Manic and Mixed Episodes Associated with Bipolar I Disorder

The safety and effectiveness of VRAYLAR for treatment of manic and mixed episodes associated with bipolar I disorder have been established in pediatric patients 10 years of age and older. Use of VRAYLAR in this population is supported by evidence from adequate and well-controlled studies in adults with manic and mixed episodes associated with bipolar I disorder, pharmacokinetic data from adult and pediatric patients, and safety data in pediatric patients 10 to 17 years of age [see Warnings and Precautions (5.7), Adverse Reactions (6.1), Clinical Pharmacology (12.3)]. The safety and effectiveness of VRAYLAR for the treatment of manic and mixed episodes associated with bipolar I disorder have not been established in pediatric patients less than 10 years of age.

Bipolar Depression

The safety and effectiveness of VRAYLAR for treatment of bipolar depression in pediatric patients have not been established.

Adjunctive Therapy for Treatment of MDD

The safety and effectiveness of VRAYLAR as adjunctive therapy for treatment of MDD in pediatric patients have not been established. Antidepressants increased the risk of suicidal thoughts and behaviors in pediatric patients [see Boxed Warning, Warnings and Precautions (5.2)].

Irritability Associated with Autism Spectrum Disorder

The safety and effectiveness of VRAYLAR for the treatment of irritability associated with autism spectrum disorder in pediatric patients have not been established.

In a single, 8-week, double-blind, placebo-controlled, flexible-dose clinical study conducted in pediatric patients 5 to 17 years of age with irritability associated with autism spectrum disorder diagnosed by the Diagnostic and Statistical Manual of Mental Disorders, 5th Edition [DSM-5] criteria, a total of 161 patients were enrolled, of which 76 patients received cariprazine and 79 received placebo. In this study, patients 5 to 9 years of age who were randomized to active treatment received cariprazine oral solution, which is not an approved formulation. Somnolence, including sedation, occurred in 18% of cariprazine-treated compared to 1% of placebo-treated pediatric patients and was observed at a higher rate than reported in other VRAYLAR studies evaluating adult patients. The mean increase in age-and-sex adjusted body weight z-score from baseline to last visit was 0.2 for cariprazine-treated versus less than 0.1 for placebo-treated pediatric patients. Increases in age- and sex-adjusted body weight z-score of at least 0.5 SD from baseline was higher in cariprazine-treated versus placebo-treated pediatric patients (19% versus 1%).

In a long term, open-label study in pediatric patients 5 to 17 years of age with irritability associated with autism spectrum disorder, the mean change in weight from baseline to last available visit was 5.3 kg; two patients discontinued due to increased weight. When body weight was adjusted for age and sex, the mean z-score change from baseline to last visit was 0.4 for cariprazine-treated patients, and 32% of patients had an increase in age- and sex-adjusted body weight z-score of at least 0.5 SD from baseline.

Juvenile Animal Studies

Juvenile rats were administered cariprazine at doses of 1, 3 and 10 mg/kg/day by oral gavage from days 28 to 90 of age, followed by an 8-week recovery (non-dosing) period. At 10 mg/kg/day, there were decreases in growth (decreased body weight and bone mass in both sexes and altered bone geometry and size in males), microscopic findings in the lung suggestive of phospholipidosis, and increased motor activity, which persisted following dose cessation. In addition, impaired learning and memory performance was observed during the dosing period, however, this effect did not persist following dose cessation. Microscopic findings in the mammary gland and/or reproductive tract (vagina, uterus and ovary) at ≥1 mg/kg/day and altered findings in the adrenal gland at doses ≥3 mg/kg/day were considered secondary to the increase in prolactin levels and were consistent with findings observed in adult rats. The no observed adverse effect level (NOAEL) was 3 mg/kg/day which is associated with systemic exposures approximately equal to clinical exposures produced at the maximum recommended pediatric dose of 4.5 mg/day based on AUC of total cariprazine.

Juvenile dogs were administered cariprazine at doses of 1, 3 and 6 mg/kg/day by oral gavage from weeks 13 to 39 of age, followed by a 4-week recovery (non-dosing) period. At doses ≥1 mg/kg/day, CNS clinical signs of decreased activity, lack of coordination, and reduced food intake were observed. At doses ≥3 mg/kg/day reversible effects on growth and non-reversible lens opacities/lens degeneration, that were not associated with retinal changes, were observed. The NOAEL was 1 mg/kg/day which is associated with systemic exposures approximately equal to clinical exposures produced at the maximum recommended pediatric dose of 4.5 mg/day based on AUC of total cariprazine.

8.5 Geriatric Use

Clinical trials of VRAYLAR did not include sufficient numbers of patients aged 65 and older to determine whether or not they respond differently from younger patients. In general, dose selection for an elderly patient should be cautious, usually starting at the low end of the dosing range, reflecting the greater frequency of decreased hepatic, renal, or cardiac function, and of concomitant disease or other drug therapy.

Antipsychotic drugs increase the risk of death in elderly patients with dementia-related psychosis. VRAYLAR is not approved for the treatment of patients with dementia-related psychosis [see Boxed Warning and Warnings and Precautions (5.1, 5.3)].

8.6 Hepatic Impairment

No dosage adjustment for VRAYLAR is required in patients with mild to moderate hepatic impairment (Child-Pugh score between 5 and 9) [see Clinical Pharmacology (12.3)]. Usage of VRAYLAR is not recommended in patients with severe hepatic impairment (Child-Pugh score between 10 and 15). VRAYLAR has not been evaluated in this patient population.

8.7 Renal Impairment

No dosage adjustment for VRAYLAR is required in patients with mild to moderate (CrCL ≥ 30 mL/minute) renal impairment [see Clinical Pharmacology (12.3)].

Usage of VRAYLAR is not recommended in patients with severe renal impairment (CrCL < 30 mL/minute). VRAYLAR has not been evaluated in this patient population.

8.8 Other Specific Populations

No dosage adjustment is required based on patient’s age, sex, or race. These factors do not affect the pharmacokinetics of VRAYLAR [see Clinical Pharmacology (12.3)].

9 DRUG ABUSE AND DEPENDENCE

9.1 Controlled Substance

VRAYLAR is not a controlled substance.

9.2 Abuse

VRAYLAR has not been systematically studied in animals or humans for its abuse potential or its ability to induce tolerance.

9.3 Dependence

VRAYLAR has not been systematically studied in animals or humans for its potential for physical dependence.

10 OVERDOSAGE

10.1 Human Experience

In pre-marketing clinical trials involving VRAYLAR in approximately 5000 patients or healthy subjects, accidental acute overdosage (48 mg/day) was reported in one patient. This patient experienced orthostasis and sedation. The patient fully recovered the same day.

10.2 Management of Overdosage

No specific antidotes for VRAYLAR are known. In managing overdose, provide supportive care, including close medical supervision and monitoring, and consider the possibility of multiple drug involvement. In case of an overdose, consult a Certified Poison Control Center (1-800-222-1222) for up-to-date guidance and advice.

11. DESCRIPTION

The active ingredient of VRAYLAR is cariprazine, an atypical antipsychotic, in hydrochloride salt form. The chemical name is trans-N-{4-[2-[4-(2,3-dichlorophenyl)piperazine-1-yl]ethyl]cyclohexyl}-N’,N’-dimethylurea hydrochloride; its empirical formula is C21H32Cl2N4O•HCl and its molecular weight is 463.9 g/mol. The chemical structure is:

VRAYLAR capsules are intended for oral administration only. Each hard gelatin capsule contains 0.5, 0.75, 1.5, 3, 4.5, or 6 mg of cariprazine base (equivalent to 0.545 mg, 0.818 mg, 1.635 mg , 3.27 mg, 4.905 mg, or 6.54 mg cariprazine HCl). In addition, capsules include the following inactive ingredients: gelatin, magnesium stearate, pregelatinized starch, shellac, and titanium dioxide. Colorants include black iron oxide (0.5, 0.75, 1.5, 3, and 6 mg), FD&C Blue 1 (0.5, 0.75, 3, 4.5, and 6 mg), FD&C Red 3 (6 mg), FD&C Red 40 (3 and 4.5 mg), or yellow iron oxide (0.5, 3, and 4.5 mg).

12. CLINICAL PHARMACOLOGY

12.1 Mechanism of Action

The mechanism of action of cariprazine is unknown. However, the efficacy of cariprazine could be mediated through a combination of partial agonist activity at central dopamine D2 and serotonin 5-HT1A receptors and antagonist activity at serotonin 5-HT2A receptors. Cariprazine forms two major metabolites, desmethylcariprazine (DCAR) and didesmethylcariprazine (DDCAR), that have in vitro receptor binding profiles similar to the parent drug.

12.2 Pharmacodynamics

Cariprazine acts as a partial agonist at the dopamine D3 and D2 receptors with high binding affinity (Ki values 0.085 nM, and 0.49 nM (D2L) and 0.69 nM (D2S), respectively) and at the serotonin 5-HT1A receptors (Ki value 2.6 nM). Cariprazine acts as an antagonist at 5-HT2B and 5-HT2A receptors with high and moderate binding affinity (Ki values 0.58 nM and 18.8 nM respectively) as well as it binds to the histamine H1 receptors (Ki value 23.2 nM). Cariprazine shows lower binding affinity to the serotonin 5-HT2C and α1A- adrenergic receptors (Ki values 134 nM and 155 nM, respectively) and has no appreciable affinity for cholinergic muscarinic receptors (IC50>1000 nM).

Effect on QTc Interval

At a dose three times the maximum recommended dose, cariprazine does not prolong the QTc interval to clinically relevant extent.

12.3 Pharmacokinetics

VRAYLAR activity is thought to be mediated by cariprazine and its two major active metabolites, desmethylcariprazine (DCAR) and didesmethylcariprazine (DDCAR), which are pharmacologically equipotent to cariprazine.

After multiple dose administration of VRAYLAR, mean cariprazine and DCAR concentrations reached steady state at around Week 1 to Week 2 and mean DDCAR concentrations appeared to be approaching steady state at around Week 4 to Week 8 in a 12-week study (Figure 1). The half-lives based on time to reach steady state, estimated from the mean concentration-time curves, are 2 to 4 days for cariprazine, about 1 to 2 days for DCAR, and approximately 1 to 3 weeks for DDCAR. The time to reach steady state for the major active metabolite DDCAR was variable across patients, with some patients not achieving steady state at the end of the 12 week treatment [see Dosage and Administration (2.1), Warnings and Precautions (5.6)]. Mean concentrations of DCAR and DDCAR are approximately 30% and 400%, respectively, of cariprazine concentrations by the end of 12-week treatment.

After discontinuation of VRAYLAR, cariprazine, DCAR, and DDCAR plasma concentrations declined in a multi-exponential manner. Mean plasma concentrations of DDCAR decreased by about 50% 1 week after the last dose, and mean cariprazine and DCAR concentration dropped by about 50% in about 1 day. There was an approximately 90% decline in plasma exposure within 1 week for cariprazine and DCAR, and at about 4 weeks for DDCAR. Following a single dose of 1 mg of cariprazine administration, DDCAR remained detectable 8 weeks post-dose.

After multiple dosing of VRAYLAR, plasma exposure of cariprazine, DCAR, and DDCAR increases approximately proportionally over the therapeutic dose range.

Figure 1. Plasma Concentration (Mean ± SE)-Time Profile During and Following
12-weeks of Treatment with Cariprazine 6 mg/daya

a Trough concentrations shown during treatment with cariprazine 6 mg/day.

SE: standard error; TOTAL CAR: sum concentration of cariprazine, DCAR and DDCAR; CAR: cariprazine

Absorption

After single dose administration of VRAYLAR, the peak plasma cariprazine concentration occurred in approximately 3-6 hours.

Administration of a single dose of 1.5 mg VRAYLAR capsule with a high-fat meal did not significantly affect the Cmax and AUC of cariprazine or DCAR.

Distribution

Cariprazine and its major active metabolites are highly bound (91 to 97%) to plasma proteins.

Elimination

Metabolism

Cariprazine is extensively metabolized by CYP3A4 and, to a lesser extent, by CYP2D6 to DCAR and DDCAR. DCAR is further metabolized into DDCAR by CYP3A4 and CYP2D6. DDCAR is then metabolized by CYP3A4 to a hydroxylated metabolite.

Excretion

Following administration of 12.5 mg/day cariprazine to patients with schizophrenia for 27 days, about 21% of the daily dose was found in urine, with approximately 1.2% of the daily dose excreted in urine as unchanged cariprazine.

Studies in Specific Populations

Patients with Hepatic Impairment

Compared to healthy subjects, exposure (Cmax and AUC) in patients with either mild or moderate hepatic impairment (Child-Pugh score between 5 and 9) was approximately 25% higher for cariprazine and 20% to 30% lower for the major metabolites (DCAR and DDCAR) following daily doses of 0.5 mg cariprazine for 14 days [see Use in Specific Populations (8.6)].

Patients with Renal Impairment

Cariprazine and its major active metabolites are minimally excreted in urine. Pharmacokinetic analyses indicated no significant relationship between plasma clearance and creatinine clearance [see Use in Specific Populations (8.7)].

CYP2D6 Poor Metabolizers

CYP2D6 poor metabolizer status does not have clinically relevant effect on pharmacokinetics of cariprazine, DCAR, or DDCAR.

Age, Sex, Race

Age, sex, or race does not have clinically relevant effect on pharmacokinetics of cariprazine, DCAR, or DDCAR in adult population.

Pediatric

Pharmacokinetics of cariprazine, DCAR, or DDCAR have been evaluated in pediatric patients (10 to 17 years of age) administered cariprazine (0.5 mg to 6 mg). Population PK analysis indicated steady-state systemic exposures (Cmax and AUCtau) of total cariprazine were up to 32% and 33% higher, respectively, in pediatric patients 10 to 12 years of age, and up to 10% and 11% higher, respectively, in pediatric patients 13 to 17 years of age, respectively, than those in adult patients receiving the same dose.

Drug Interaction Studies

In vitro studies

Cariprazine and its major active metabolites did not induce CYP1A2 and CYP3A4 enzymes and were weak inhibitors of CYP1A2, CYP2C9, CYP2D6, and CYP3A4 in vitro. Cariprazine was also a weak inhibitor of CYP2C19, CYP2A6, and CYP2E1 in vitro.

Cariprazine and its major active metabolites are not substrates of P-glycoprotein (P-gp), the organic anion transporting polypeptides 1B1 and 1B3 (OATP1B1 and OATP1B3), or the breast cancer resistance protein (BCRP).

Cariprazine and its major active metabolites were poor or non-inhibitors of transporters OATP1B1, OATP1B3, BCRP, organic cation transporter 2 (OCT2), and organic anion transporters 1 and 3 (OAT1 and OAT3) in vitro. The major active metabolites were also poor or non-inhibitors of transporter P-gp although cariprazine was probably a P-gp inhibitor based on the theoretical GI concentrations at high doses in vitro.

Based on in vitro studies, VRAYLAR is unlikely to cause clinically significant pharmacokinetic drug interactions with substrates of CYP1A2, CYP2A6, CYP2C9, CYP2C19, CYP2D6, CYP2E, and CYP3A4, or OATP1B1, OATP1B3, BCRP, OCT2, OAT1 and OAT3.

In vivo studies and Model-based Approaches

CYP3A4 inhibitors

In the clinical drug-drug interaction studies, co-administration of ketoconazole (400 mg/day for four days), a strong CYP3A4 inhibitor, with VRAYLAR (0.5 mg/day) increased total cariprazine (the sum of cariprazine, DCAR and DDCAR) Cmax and AUC0-24h by approximately 100%. Co-administration of erythromycin (500 mg twice daily for 21 days), a moderate CYP3A4 inhibitor, with VRAYLAR (1.5 mg/day) increased total cariprazine Cmax and AUC0-24h by approximately 50%.

Physiologically based pharmacokinetic model-based analyses suggest that co-administration of ketoconazole (400 mg/day) with VRAYLAR (0.5 mg/day) at steady state is predicted to result in up to about 5.5-fold and 6-fold increase in Cmax and AUC0-24h, respectively, of total cariprazine. Co-administration of fluconazole (200 mg/day), a moderate CYP3A inhibitor, with VRAYLAR (0.5 mg/day) at steady state is predicted to result in up to about 3-fold increase in Cmax and AUC0-24h of total cariprazine.

CYP3A4 inducers

CYP3A4 is responsible for the formation and elimination of the active metabolites of cariprazine. The effect of CYP3A4 inducers on the plasma exposure of cariprazine and its major active metabolites has not been evaluated, and the net effect is unclear.

CYP2D6 inhibitors

CYP2D6 inhibitors are not expected to influence pharmacokinetics of cariprazine, DCAR, or DDCAR based on the observations in CYP2D6 poor metabolizers.

Proton pump inhibitors

Co-administration of pantoprazole (40 mg/day), a proton pump inhibitor, with VRAYLAR (6 mg/day) in patients with schizophrenia for 15 days did not affect cariprazine exposure at steady-state, based on Cmax and AUC0-24. Similarly, no significant change in exposure to DCAR and DDCAR was observed.

13 NONCLINICAL TOXICOLOGY

13.1 Carcinogenesis, Mutagenesis, Impairment of Fertility

Carcinogenesis

There was no increase in the incidence of tumors following daily oral administration of cariprazine to rats for 2 years and to Tg.rasH2 mice for 6 months at doses which are up to 4 and 19 times respectively, the MRHD of 6 mg/day based on AUC of total cariprazine, (i.e. sum of AUC values of cariprazine, DCAR and DDCAR).

Rats were administered cariprazine at oral doses of 0.25, 0.75, and 2.5 (males)/1, 2.5, and 7.5 mg/kg/day (females) which are 0.2 to 1.8 (males)/ 0.8 to 4.1 (females) times the MRHD of 6 mg/day based on AUC of total cariprazine.

Tg.rasH2 mice were administered cariprazine at oral doses of 1, 5, and 15 (males)/5, 15, and 50 mg/kg/day (females) which are 0.2 to 7.9 (males)/2.6 to 19 (females) times the MRHD of 6 mg/day based on AUC of total cariprazine.

Mutagenesis

Cariprazine was not mutagenic in the in vitro bacterial reverse mutation assay, nor clastogenic in the in vitro human lymphocyte chromosomal aberration assay or in the in vivo mouse bone marrow micronucleus assay. However, cariprazine increased the mutation frequency in the in vitro mouse lymphoma assay under conditions of metabolic activation. The major human metabolite DDCAR was not mutagenic in the in vitro bacterial reverse mutation assay, however, it was clastogenic and induced structural chromosomal aberration in the in vitro human lymphocyte chromosomal aberration assay.

Impairment of Fertility

Cariprazine was administered orally to male and female rats before mating, through mating, and up to day 7 of gestation at doses of 1, 3, and 10 mg/kg/day which are 1.6 to 16 times the MRHD of 6 mg/day based on mg/m^2. In female rats, lower fertility and conception indices were observed at all dose levels which are equal to or higher than 1.6 times the MRHD of 6 mg/day based on mg/m^2. No effects on male fertility were noted at any dose up to 4.3 times the MRHD of 6 mg/day based on AUC of total cariprazine.

13.2 Animal Toxicology and/or Pharmacology

Cariprazine caused bilateral cataract and cystic degeneration of the retina in the dog following oral daily administration for 13 weeks and/or 1 year and retinal degeneration/atrophy in the rat following oral daily administration for 2 years. Cataract in the dog was observed at 4 mg/kg/day which is 7.1 (male) and 7.7 (female) times the MRHD of 6 mg/day based on AUC of total cariprazine. The NOEL for cataract and retinal toxicity in the dog is 2 mg/kg/day which is 5 (males) to 3.6 (females) times the MRHD of 6 mg/day based on AUC of total cariprazine. Increased incidence and severity of retinal degeneration/atrophy in the rat occurred at all doses tested, including the low dose of 0.75 mg/kg/day, at total cariprazine plasma levels less than clinical exposure (AUC) at the MRHD of 6 mg/day. Cataract was not observed in other repeat dose studies in pigmented mice or albino rats.

Phospholipidosis was observed in the lungs of rats, dogs, and mice (with or without inflammation) and in the adrenal gland cortex of dogs at clinically relevant exposures (AUC) of total cariprazine. Phospholipidosis was not reversible at the end of the 1-2 month drug-free periods. Inflammation was observed in the lungs of dogs dosed daily for 1 year with a NOEL of 1 mg/kg/day which is 2.7 (males) and 1.7 (females) times the MRHD of 6 mg/day based on AUC of total cariprazine. No inflammation was observed at the end of 2-month drug free period following administration of 2 mg/kg/day which is 5 (males) and 3.6 (females) times the MRHD of 6 mg/day based on AUC of total cariprazine; however, inflammation was still present at higher doses.

Hypertrophy of the adrenal gland cortex was observed at clinically relevant total cariprazine plasma concentrations in rats (females only) and mice following daily oral administration of cariprazine for 2 years and 6 months, respectively. Reversible hypertrophy/hyperplasia and vacuolation/vesiculation of the adrenal gland cortex were observed following daily oral administration of cariprazine to dogs for 1 year. The NOEL was 2 mg/kg/day which is 5 (males) and 3.6 (females) times the MRHD of 6 mg/day based on AUC of total cariprazine. The relevance of these findings to human risk is unknown.

14 CLINICAL STUDIES

14.1 Schizophrenia

The efficacy of VRAYLAR for the treatment of schizophrenia in adult patients was established in three, 6-week, randomized, double-blind, placebo-controlled trials in patients (mean age of 37 years, aged 18 to 60 years; 31% were female; and 45% were Caucasian) who met Diagnostic and Statistical Manual of Mental Disorders 4th edition, Text Revision (DSM-IV-TR) criteria for schizophrenia. An active control arm (risperidone or aripiprazole) was included in two trials to assess assay sensitivity. In all three trials, VRAYLAR was superior to placebo.

Positive and Negative Syndrome Scale (PANSS) and Clinical Global Impressions-Severity (CGI-S) rating scales were used as the primary and secondary efficacy measures, respectively, for assessing psychiatric signs and symptoms in each trial:

- PANSS is a 30-item scale that measures positive symptoms of schizophrenia (7 items), negative symptoms of schizophrenia (7 items), and general psychopathology (16 items), each rated on a scale of 1 (absent) to 7 (extreme). The PANSS total score may range from 30 to 210 with the higher score reflecting greater severity.
- The CGI-S is a validated clinician-related scale that measures the patient’s current illness state and overall clinical state on a 1 (normal, not at all ill) to 7-point (extremely ill) scale.

In each study, the primary endpoint was change from baseline in PANSS total score at the end of week 6. The change from baseline for VRAYLAR and active control groups was compared to placebo. The results of the trials are shown in Table 16. The time course of efficacy results of Study 2 is shown in Figure 2.

Study 1: In a 6-week, placebo-controlled trial (N = 711) involving three fixed doses of VRAYLAR (1.5, 3, or 4.5 mg/day) and an active control (risperidone), all VRAYLAR doses and the active control were superior to placebo on the PANSS total score and the CGI-S.

Study 2: In a 6-week, placebo-controlled trial (N = 604) involving two fixed doses of VRAYLAR (3 or 6 mg/day) and an active control (aripiprazole), both VRAYLAR doses and the active control were superior to placebo on the PANSS total score and the CGI-S.

Study 3: In a 6-week, placebo-controlled trial (N = 439) involving two flexible-dose range groups of VRAYLAR (3 to 6 mg/day or 6 to 9 mg/day), both VRAYLAR groups were superior to placebo on the PANSS total score and the CGI-S.

The efficacy of VRAYLAR was demonstrated at doses ranging from 1.5 to 9 mg/day compared to placebo. There was, however, a dose-related increase in certain adverse reactions, particularly above 6 mg. Therefore, the maximum recommended dose is 6 mg/day.

Examination of population subgroups based on age (there were few patients over 55), sex, and race did not suggest any clear evidence of differential responsiveness.

Table 16. Primary Analysis Results from Schizophrenia Trials
Study Number | Treatment Group (# ITT patients) | Primary Efficacy Endpoint: PANSS Total
 |  | Mean Baseline Score (SD) | LS Mean Change from Baseline (SE) | Placebo-subtracted Differencea (95% CI)
Study 1 | VRAYLAR (1.5 mg/day)* (n=140) | 97.1 (9.1) | -19.4 (1.6) | -7.6 (-11.8, -3.3)
 | VRAYLAR (3 mg/day)* (n=140) | 97.2 (8.7) | -20.7 (1.6) | -8.8 (-13.1, -4.6)
 | VRAYLAR (4.5 mg/day)* (n=145) | 96.7 (9.0) | -22.3 (1.6) | -10.4 (-14.6, -6.2)
 | Placebo (n=148) | 97.3 (9.2) | -11.8 (1.5) | --
Study 2 | VRAYLAR (3 mg/day)* (n=151) | 96.1 (8.7) | -20.2 (1.5) | -6.0 (-10.1, -1.9)
 | VRAYLAR (6 mg/day)* (n=154) | 95.7 (9.4) | -23.0 (1.5) | -8.8 (-12.9, -4.7)
 | Placebo (n=149) | 96.5 (9.1) | -14.3 (1.5) | --
Study 3 | VRAYLAR (3-6 mg/day)* (n=147) | 96.3 (9.3) | -22.8 (1.6) | -6.8 (-11.3, -2.4)
 | VRAYLAR (6-9 mg/day)*b (n=147) | 96.3 (9.0) | -25.9 (1.7) | -9.9 (-14.5, -5.3)
 | Placebo (n=145) | 96.6 (9.3) | -16.0 (1.6) | --
ITT: intent-to-treat; SD: standard deviation; SE: standard error; LS Mean: least-squares mean; CI: unadjusted confidence interval
aDifference (drug minus placebo) in least-squares mean change from baseline
*Doses that are statistically significantly superior to placebo
bThe maximum recommended daily dose is 6 mg. Doses above 6 mg daily do not confer increased effectiveness sufficient to outweigh dose-related adverse reactions.

Figure 2. Change from Baseline in PANSS total score by weekly visits (Study 2)

The safety and efficacy of VRAYLAR as maintenance treatment in adult patients with schizophrenia were demonstrated in a randomized withdrawal trial that included 200 patients meeting DSM-IV criteria for schizophrenia who were clinically stable following 20 weeks of open-label cariprazine at doses of 3 to 9 mg/day. Patients were randomized to receive either placebo or cariprazine at the same dose for up to 72 weeks for observation of relapse. The primary endpoint was time to relapse. Relapse during the double-blind phase (DBP) was defined as meeting any one of the following criteria: hospitalization due to worsening of schizophrenia, increase in the PANSS total score by ≥ 30%, increase in CGI-S score by ≥ 2 points, deliberate self-injury, aggressive or violent behavior, clinically significant suicidal or homicidal ideation, or score >4 on one or more of the following PANSS items: delusions (P1), conceptual disorganization (P2), hallucination (P3), suspiciousness or persecution (P6), hostility (P7), uncooperativeness (G8), or poor impulse control (G14).

The efficacy of VRAYLAR was demonstrated at doses ranging from 3 to 9 mg/day compared to placebo. There was, however, a dose-related increase in certain adverse reactions, particularly above 6 mg. Therefore, the maximum recommended dose is 6 mg/day.

The Kaplan-Meier curves of the time to relapse during the double-blind, placebo-controlled, randomized withdrawal phase of the long-term trial are shown in Figure 3. Time to relapse was statistically significantly longer in the VRAYLAR-treated group compared to the placebo group.

Figure 3. Kaplan-Meier Curves of Cumulative Rate of Relapse During the Double-Blind Treatment Period

DB = double-blind
*The maximum recommended daily dose is 6 mg. Doses above 6 mg daily do not confer increased effectiveness sufficient to outweigh dose-related adverse reactions.

14.2 Manic or Mixed Episodes Associated with Bipolar I Disorder

The efficacy of VRAYLAR in the acute treatment of bipolar mania in adult patients was established in three, 3-week placebo-controlled trials in patients (mean age of 39 years, range 18 to 65 years; 40% were female; and 48% were Caucasian) who met DSM-IV-TR criteria for bipolar 1 disorder with manic or mixed episodes with or without psychotic features. In all three trials, VRAYLAR was superior to placebo.

Young Mania Rating Scale (YMRS) and Clinical Global Impressions-Severity scale (CGI-S) were used as the primary and secondary efficacy measures, respectively, for assessing psychiatric signs and symptoms in each trial:

- The YMRS is an 11-item clinician-rated scale traditionally used to assess the degree of manic symptomatology. YMRS total score may range from 0 to 60 with a higher score reflecting greater severity.
- The CGI-S is validated clinician-related scale that measures the patient’s current illness state and overall clinical state on a 1 (normal, not at all ill) to 7-point (extremely ill) scale.

In each study, the primary endpoint was decrease from baseline in YMRS total score at the end of week 3. The change from baseline for each VRAYLAR dose group was compared to placebo. The results of the trials are shown in Table 17. The time course of efficacy results is shown in Figure 4.

Study 4: In a 3-week, placebo-controlled trial (N = 492) involving two flexible-dose range groups of VRAYLAR (3 to 6 mg/day or 6 to 12 mg/day), both VRAYLAR dose groups were superior to placebo on the YMRS total score and the CGI-S. The 6 to 12 mg/day dose group showed no additional advantage.

Study 5: In a 3-week, placebo-controlled trial (N = 235) involving a flexible-dose range of VRAYLAR (3 to 12 mg/day), VRAYLAR was superior to placebo on the YMRS total score and the CGI-S.

Study 6: In a 3-week, placebo-controlled trial (N = 310) involving a flexible-dose range of VRAYLAR (3 to 12 mg/day), VRAYLAR was superior to placebo on the YMRS total score and the CGI-S.

The efficacy of VRAYLAR was established at doses ranging from 3 to 12 mg/day. Doses above 6 mg did not appear to have additional benefit over lower doses (Table 17), and there was a dose-related increase in certain adverse reactions. Therefore, the maximum recommended dose is 6 mg/day.

Examination of population subgroups based on age (there were few patients over 55), sex, and race did not suggest any clear evidence of differential responsiveness.

Table 17. Primary Analysis Results from Manic or Mixed Episodes Associated with Bipolar I Disorder Trials
Study Number | Treatment Group (# ITT patients) | Primary Efficacy Endpoint: YMRS Total
 |  | Mean Baseline Score (SD) | LS Mean Change from Baseline (SE) | Placebo-subtracted Differencea (95% CI)
Study 4 | VRAYLAR (3-6 mg/day)* (n=165) | 33.2 (5.6) | -18.6 (0.8) | -6.1 (-8.4, -3.8)
 | VRAYLAR (6-12 mg/day)*b (n=167) | 32.9 (4.7) | -18.5 (0.8) | -5.9 (-8.2, -3.6)
 | Placebo (n=160) | 32.6 (5.8) | -12.5 (0.8) | --
Study 5 | VRAYLAR (3-12 mg/day)*b (n=118) | 30.6 (5.0) | -15.0 (1.1) | -6.1 (-8.9, -3.3)
 | Placebo (n=117) | 30.2 (5.2) | -8.9 (1.1) | --
Study 6 | VRAYLAR (3-12 mg/day)*b (n=158) | 32.3 (5.8) | -19.6 (0.9) | -4.3 (-6.7, -1.9)
 | Placebo (n=152) | 32.1 (5.6) | -15.3 (0.9) | --
ITT: intent-to-treat; SD: standard deviation; SE: standard error; LS Mean: least-squares mean; CI: unadjusted confidence interval
aDifference (drug minus placebo) in least-squares mean change from baseline
*Doses that are statistically significantly superior to placebo
bThe maximum recommended daily dose is 6 mg. Doses above 6 mg daily do not confer increased effectiveness sufficient to outweigh dose-related adverse reactions.

Figure 4. Change from Baseline in YMRS total score by study visit (Study 4)

* The maximum recommended daily dose is 6 mg. Doses above 6 mg daily do not confer increased effectiveness sufficient to outweigh dose-related adverse reactions.

14.3 Depressive Episodes Associated with Bipolar I Disorder (Bipolar Depression)

The efficacy of VRAYLAR in the treatment of depressive episodes associated with bipolar I disorder (bipolar depression) in adult patients was established in one 8-week and two 6-week placebo-controlled trials in patients (mean age of 43 years, range 18 to 65 years; 61% were female; and 75% were Caucasian) who met DSM-IV-TR or DSM-5 criteria for depressive episodes associated with bipolar I disorder.

In each study, the primary endpoint was change from baseline in Montgomery-Asberg Depression Rating Scale (MADRS) total score at the end of Week 6. The MADRS is a 10-item clinician-rated scale with total scores ranging from 0 (no depressive features) to 60 (maximum score). The MADRS total score change from baseline for VRAYLAR compared to placebo is shown in Table 18. The time course of efficacy results of Study 8 is shown in Figure 5. In each study, the VRAYLAR 1.5 mg dose demonstrated statistical significance over placebo. The secondary endpoint was change from baseline to Week 6 in CGI-S. The CGI-S is validated clinician-related scale that measures the patient’s current illness state and overall clinical state on a 1 (normal, not at all ill) to 7-point (extremely ill) scale.

Study 7: In an 8-week, placebo-controlled trial (N = 571) involving three-fixed doses of VRAYLAR (0.75 mg/day, 1.5 mg/day, and 3 mg/day), VRAYLAR 1.5 mg was superior to placebo at end of Week 6 on the MADRS total score and the CGI-S.

Study 8: In a 6-week, placebo-controlled trial (N = 474) involving two-fixed doses of VRAYLAR (1.5 mg/day and 3 mg/day), VRAYLAR 1.5 mg and 3 mg were superior to placebo at end of Week 6 on the MADRS total score.

Study 9: In a 6-week, placebo-controlled trial (N = 478) involving two-fixed doses of VRAYLAR (1.5 mg/day and 3 mg/day), VRAYLAR 1.5 mg was superior to placebo at end of Week 6 on the MADRS total score and the CGI-S.

Examination of population subgroups based on age (there were few patients over 55), sex, and race did not suggest any clear evidence of differential responsiveness.

Table 18. Primary Analysis Results from Bipolar Depression Trials
Study Number | Treatment Group (# ITT patients) | Primary Efficacy Endpoint: MADRS Total
 |  | Mean Baseline Score (SD) | LS Mean Change from Baseline (SE) | Placebo-subtracted Differencea (95% CI)
Study 7 | VRAYLAR (1.5 mg/day)* (n=145) VRAYLAR (3 mg/day) (n=145) Placebo (n=141) | 30.3 (4.4) 30.6 (4.7) 30.4 (4.6) | -15.1 (0.8) -13.7 (0.9) -11.1 (0.9) | -4.0 (-6.3, -1.6) -2.5 (-4.9, -0.1)
Study 8 | VRAYLAR (1.5 mg/day)* (n=154) | 30.7 (4.3) | -15.1 (0.8) | -2.5 (-4.6, -0.4)
 | VRAYLAR (3 mg/day)* (n=164) | 31.0 (4.9) | -15.6 (0.8) | -3.0 (-5.1, -0.9)
 | Placebo (n=156) | 30.2 (4.4) | -12.6 (0.8)
Study 9 | VRAYLAR (1.5 mg/day)* (n=162) | 31.5 (4.3) | -14.8 (0.8) | -2.5 (-4.6, -0.4)
 | VRAYLAR (3 mg/day) (n=153) | 31.5 (4.8) | -14.1 (0.8) | -1.8 (-3.9, 0.4)
 | Placebo (n=163) | 31.4 (4.5) | -12.4 (0.8)
ITT: intent-to-treat; SD: standard deviation; SE: standard error; LS Mean: least-squares mean; CI: confidence interval
aDifference (drug minus placebo) in least-squares mean change from baseline
*Doses that are statistically significantly superior to placebo

Figure 5. LS Mean* Change from Baseline in MADRS Total Score by Visits (Study 8)

*LS Mean: least-squares mean

14.4 Adjunctive Treatment of Major Depressive Disorder

The efficacy of VRAYLAR as adjunctive therapy to antidepressants for the treatment of major depressive disorder (MDD) was evaluated in 2 trials in adult patients (mean age of 45 years, range 18 to 65 years; 72% were female; and 85% were Caucasian) who met DSM-IV-TR or DSM-5 criteria for MDD, with or without symptoms of anxiety, who had an inadequate response to 1 to 3 courses of prior antidepressant (ADT) therapy. Inadequate response during antidepressant treatment was defined as less than 50% improvement to antidepressant treatment of adequate dose and adequate duration.

In each study, the primary endpoint was change from baseline to Week 6 (Study 10) or Week 8 (Study 11) in the Montgomery-Asberg Depression Rating Scale (MADRS) total score, a 10-item clinician-rated scale used to assess the degree of depressive symptomatology, with 0 representing no symptoms and 60 representing worst symptoms.

Study 10: In a 6-week, placebo-controlled trial (N = 751) involving two fixed doses of VRAYLAR (1.5 mg per day or 3 mg per day) + ADT, VRAYLAR 1.5 mg + ADT was superior to placebo + ADT at end of Week 6 on the MADRS total score. The treatment effect in the VRAYLAR 3 mg per day + ADT group (vs. placebo + ADT) was not statistically significant.

Study 11: An 8-week, placebo-controlled trial (N = 808) involved flexible doses of VRAYLAR 1 to 2 mg per day + ADT or 2 to 4.5 mg per day + ADT. VRAYLAR 2 to 4.5 mg (mean dose was 2.6 mg) + ADT was superior to placebo + ADT at end of Week 8 on the MADRS total score. The treatment effect in the VRAYLAR 1 to 2 mg per day + ADT group (vs. placebo + ADT) was not statistically significant.

Results from the primary efficacy parameters for both trials (Studies 10 and 11) are shown below in Table 19. Figure 6 below shows the time course of response based on the primary efficacy measure (MADRS total score) in Study 10.

Table 19: Primary Analysis Results from Adjunctive Treatment of Major Depressive Disorder Trials
Study Number | Treatment Group (# ITT patients) | Primary Efficacy Endpoint: MADRS Total Score
 |  | Mean Baseline Score (SD) | LS Mean Change from Baseline (SE) | Placebo-subtracted Differencea (95% CI)
Study 10 | VRAYLAR (1.5 mg/day) + ADT* (n=250) VRAYLAR (3 mg/day) + ADT (n=252) Placebo + ADT (n=249) | 32.8 (5.0) 32.7 (4.9) 31.9 (5.7) | -14.1 (0.7) -13.1 (0.7) -11.5 (0.7) | -2.5(-4.2, -0.9) -1.5 (-3.2, 0.1)
Study 11 | VRAYLAR (1 to 2 mg/day) + ADT (n=273) | 29.0 (4.3) | -13.4 (0.5) | -0.9 (-2.4, 0.6)
 | VRAYLAR (2 to 4.5 mg/day) + ADT* (n=271) | 29.3 (4.1) | -14.6 (0.6) | -2.2 (-3.7, -0.6)
 | Placebo + ADT (n=264) | 28.9 (4.3) | -12.5 (0.5)

SD: standard deviation; SE: standard error; LS Mean: least-squares mean; CI: unadjusted confidence interval
* Dosages statistically significantly superior to placebo
a Difference (drug minus placebo) in least-squares mean change from baseline

Examination of population subgroups based on age, sex, and race did not suggest any clear evidence of differential responsiveness.

Figure 6. LS Mean‡ Change from Baseline to Week 6 in MADRS Total Score in Adjunctive Treatment of Major Depressive Disorder (Study 10)

‡ LS Mean: least-squares mean

* Dose was not statistically significant.

16 HOW SUPPLIED/STORAGE AND HANDLING

16.1 How Supplied

VRAYLAR (cariprazine) capsules are supplied as follows:

Capsule Strength | Imprint Codes | Capsule Color | Package Configuration | NDC Code
0.5 mg | FL 0.5 | Ivory to yellow cap and grey to green body | Bottle of 30 | 61874-250-30
0.75 mg | FL 0.75 | Grey to green cap and blue body | Bottle of 30 | 61874-275-30
1.5 mg | FL 1.5 | White cap and body | Blister pack of 7 | 61874-115-17
 |  |  | Bottle of 30 | 61874-115-30
 |  |  | Bottle of 90 | 61874-115-90
 |  |  | Box of 20 (Hospital Unit Dose) | 61874-115-20
3 mg | FL 3 | Green to blue-green cap and white body | Bottle of 30 | 61874-130-30
 |  |  | Bottle of 90 | 61874-130-90
 |  |  | Box of 20 (Hospital Unit Dose) | 61874-130-20
4.5 mg | FL 4.5 | Green to blue-green cap and body | Bottle of 30 | 61874-145-30
 |  |  | Bottle of 90 | 61874-145-90
6 mg | FL 6 | Purple cap and white body | Bottle of 30 | 61874-160-30
 |  |  | Bottle of 90 | 61874-160-90
(1) 1.5 mg, (6) 3 mg | FL 1.5, FL 3 |  | Mixed Blister pack of 7 | 61874-170-08

16.2 Storage and Handling

Store at 20ºC to 25°C (68ºF to 77°F); excursions permitted between 15°C and 30°C (59°F and 86°F) [see USP Controlled Room Temperature]. Protect 3 mg and 4.5 mg capsules from light to prevent potential color fading.

17 PATIENT COUNSELING INFORMATION

Advise the patient or caregiver to read the FDA-approved patient labeling (Medication Guide).

Suicidal Thoughts and Behaviors

Advise patients and caregivers to look for the emergence of suicidal thoughts and behaviors, especially early during treatment and when the dosage is adjusted up or down and instruct them to report such symptoms to their healthcare provider [see Box Warning and Warnings and Precautions (5.2)].

Dosage and Administration

Advise patients that VRAYLAR can be taken with or without food. Counsel them on the importance of following dosage escalation instructions [see Dosage and Administration (2)].

Neuroleptic Malignant Syndrome (NMS)

Counsel patients about a potentially fatal adverse reaction, Neuroleptic Malignant Syndrome (NMS), that has been reported in association with administration of antipsychotic drugs. Advise patients, family members, or caregivers to contact the healthcare provider or to report to the emergency room if they experience signs and symptoms of NMS [see Warnings and Precautions (5.4)].

Tardive Dyskinesia

Counsel patients on the signs and symptoms of tardive dyskinesia and to contact their health care provider if these abnormal movements occur [see Warnings and Precautions (5.5)].

Late-Occurring Adverse Reactions

Counsel patients that adverse reactions may not appear until several weeks after the initiation of VRAYLAR treatment [see Warnings and Precautions (5.6)].

Metabolic Changes (Hyperglycemia and Diabetes Mellitus, Dyslipidemia, and Weight Gain)

Educate patients about the risk of metabolic changes, how to recognize symptoms of hyperglycemia and diabetes mellitus, and the need for specific monitoring, including blood glucose, lipids, and weight [see Warnings and Precautions (5.7)].

Leukopenia/Neutropenia

Advise patients with a pre-existing low WBC or a history of drug-induced leukopenia/neutropenia that they should have their CBC monitored while taking VRAYLAR [see Warnings and Precautions (5.8)].

Orthostatic Hypotension and Syncope

Counsel patients on the risk of orthostatic hypotension and syncope, especially early in treatment, and also at times of re-initiating treatment or increases in dose [see Warnings and Precautions (5.9)].

Interference with Cognitive and Motor Performance

Caution patients about performing activities requiring mental alertness, such as operating hazardous machinery or operating a motor vehicle, until they are reasonably certain that VRAYLAR therapy does not affect them adversely [see Warnings and Precautions (5.12)].

Heat Exposure and Dehydration

Educate patients regarding appropriate care in avoiding overheating and dehydration [see Warnings and Precautions (5.13)].

Concomitant Medications

Advise patients to notify their physicians if they are taking, or plan to take, any prescription or over-the-counter drugs since there is a potential for interactions [see Drug Interactions (7)].

Pregnancy

Advise patients that third trimester use of VRAYLAR may cause extrapyramidal and/or withdrawal symptoms in a neonate. Advise patients to notify their healthcare provider with a known or suspected pregnancy [see Use in Specific Populations (8.1)].

Pregnancy Registry

Advise patients that there is a pregnancy exposure registry that monitors pregnancy outcomes in women exposed to VRAYLAR during pregnancy [see Use in Specific Populations (8.1)].

Licensed from Gedeon Richter Plc.

Manufactured by:
Forest Laboratories Ireland Limited
Dublin, IE.

Distributed by:
AbbVie Inc.
North Chicago, IL 60064, USA

VRAYLAR and its design are trademarks of Allergan Pharmaceuticals International Limited, an AbbVie company.

© 2025 AbbVie. All rights reserved.

20093086

MEDICATION GUIDE
VRAYLAR® (VRAY-lar)
(cariprazine)
capsules

What is the most important information I should know about VRAYLAR?
VRAYLAR may cause serious side effects, including:

- Increased risk of death in elderly people with dementia related psychosis. Medicines like VRAYLAR can raise the risk of death in elderly who have lost touch with reality (psychosis) due to confusion and memory loss (dementia). VRAYLAR is not approved for the treatment of patients with dementia-related psychosis.
- Increased risk of suicidal thoughts and actions. VRAYLAR and antidepressant medicines increase the risk of suicidal thoughts or actions in people 24 years of age and younger especially within the first few months of treatment or when the dose is changed.
  ○ Depression and other mental illnesses are the most important causes of suicidal thoughts and actions.

How can I watch for and try to prevent suicidal thoughts and actions in myself or a family member?
○ Pay close attention to any changes, especially sudden changes in mood, behaviors, thoughts, or feelings. This is very important when VRAYLAR or the antidepressant medicine is started or when the dose is changed.
○ Call the healthcare provider right away to report new or sudden changes in mood, behavior, thoughts, or feelings, or if you develop suicidal thoughts or actions.
○ Keep all follow-up visits with the healthcare provider as scheduled. Call the healthcare provider between visits as needed, especially if you have concerns about symptoms.
Call a healthcare provider right away if you or your family member has any of the following symptoms, especially if they are new, worse, or worry you:

- thoughts about suicide or dying

- suicide attempts

- new or worse depression

- new or worse anxiety

- feeling very agitated or restless

- panic attacks

- trouble sleeping (insomnia)

- new or worse irritability

- acting aggressive, being angry, or violent

- acting on dangerous impulses

- an extreme increase in activity and talking
- (mania)

See “What are the possible side effects of VRAYLAR?” for more information about side effects.

- other unusual changes in behavior or mood

What is VRAYLAR?
VRAYLAR is a prescription medicine used:

- to treat schizophrenia in adults and children ages 13 years and older
- to treat short-term (acute) manic or mixed episodes that happen with bipolar I disorder in adults and children ages 10 years and older
- to treat depressive episodes that happen with bipolar I disorder (bipolar depression) in adults
- along with antidepressant medicines to treat major depressive disorder (MDD) in adults

It is not known if VRAYLAR is safe and effective to treat children:

- under 13 years of age with schizophrenia
- under 10 years of age with manic or mixed episodes that happen with bipolar I disorder
- with bipolar depression
- along with antidepressant medicines to treat MDD

Who should not take VRAYLAR?
Do not take VRAYLAR if you are allergic to cariprazine. See the end of this Medication Guide for a complete list of ingredients in VRAYLAR.

Before taking VRAYLAR, tell your healthcare provider about all of your medical conditions, including if you:

- have or had heart problems or a stroke
- have or had low or high blood pressure
- have or had diabetes or high blood sugar, or a family history of diabetes or high blood sugar
- have or had high levels of total cholesterol, LDL cholesterol, or triglycerides or low levels of HDL cholesterol
- have or had seizures (convulsions)
- have or had kidney or liver problems
- have or had a low white blood cell count
- are pregnant or plan to become pregnant. VRAYLAR may harm your unborn baby. Taking VRAYLAR during your third trimester of pregnancy may cause your baby to have abnormal muscle movements or withdrawal symptoms after birth. Talk to your healthcare provider about the risk to your unborn baby if you take VRAYLAR during pregnancy.
  ○ Tell your healthcare provider if you become pregnant or think you are pregnant during treatment with VRAYLAR.
  ○ There is a pregnancy exposure registry for women who are exposed to VRAYLAR during pregnancy. If you become pregnant during treatment with VRAYLAR, talk to your healthcare provider about registering with the National Pregnancy Registry for Atypical Antipsychotics. You can register by calling 1-866-961-2388 or go to http://womensmentalhealth.org/clinical-and-research-programs/pregnancyregistry/.
- are breastfeeding or plan to breastfeed. It is not known if VRAYLAR passes into your breast milk. Talk to your healthcare provider about the best way to feed your baby during treatment with VRAYLAR.

Tell your healthcare provider about all the medicines you take, including prescription and over-the-counter medicines, vitamins, and herbal supplements.
VRAYLAR and other medicines may affect each other causing possible serious side effects. VRAYLAR may affect the way other medicines work, and other medicines may affect how VRAYLAR works.
Your healthcare provider can tell you if it is safe to take VRAYLAR with your other medicines. Do not start or stop any medicines while taking VRAYLAR without talking to your healthcare provider first.
Know the medicines you take. Keep a list of your medicines to show your healthcare provider and pharmacist when you get a new medicine.

How should I take VRAYLAR?

- Take VRAYLAR exactly as your healthcare provider tells you to take it. Do not change the dose or stop taking VRAYLAR without first talking to your healthcare provider.
- Take VRAYLAR 1 time each day with or without food.
- If you take too much VRAYLAR, call your healthcare provider or Poison Control Center at 1-800-222-1222 or go to the nearest hospital emergency room, right away.

What should I avoid while taking VRAYLAR?

- Do not drive, operate machinery, or do other dangerous activities until you know how VRAYLAR affects you. VRAYLAR may make you drowsy.
- Do not become too hot or dehydrated during treatment with VRAYLAR.
  ○ Do not exercise too much.
  ○ In hot weather, stay inside in a cool place if possible.
  ○ Stay out of the sun.
  ○ Do not wear too much clothing or heavy clothing.
  ○ Drink plenty of water.

What are the possible side effects of VRAYLAR?
VRAYLAR may cause serious side effects, including:

- See “What is the most important information I should know about VRAYLAR?”
- Stroke (cerebrovascular problems) in elderly people with dementia-related psychosis that can lead to death.
- Neuroleptic malignant syndrome (NMS) is a serious condition that can lead to death. Call your healthcare provider or go to the nearest hospital emergency room right away if you have some or all of the following signs and symptoms of NMS:

○ high fever

○ stiff muscles

○ confusion

○ increased sweating

○ changes in your breathing, heart rate, and blood pressure

- Uncontrolled body movements (tardive dyskinesia). VRAYLAR may cause movements that you cannot control in your face, tongue, or other body parts. Tardive dyskinesia may not go away, even if you stop taking VRAYLAR. Tardive dyskinesia may also start after you stop taking VRAYLAR.
- Late occurring side effects. VRAYLAR stays in your body for a long time. Some side effects may not happen right away and can start a few weeks after you start taking VRAYLAR, or if your dose of VRAYLAR increases. Your healthcare provider should monitor you for side effects for several weeks after you start and after any increase in your dose of VRAYLAR.
- Problems with your metabolism such as:
  ○ high blood sugar (hyperglycemia) and diabetes. Increases in blood sugar can happen in some people who take VRAYLAR. Extremely high blood sugar can lead to coma or death. Your healthcare provider should check your blood sugar before you start, or soon after you start VRAYLAR, and then regularly during long-term treatment with VRAYLAR.

Call your healthcare provider if you have any of these symptoms of high blood sugar during treatment with VRAYLAR:
• feel very thirsty • need to urinate more than usual
• feel very hungry • feel weak or tired
• feel sick to your stomach • feel confused, or your breath smells fruity

- increased fat levels (cholesterol and triglycerides) in your blood. Your healthcare provider should check the fat levels in your blood before you start, or soon after you start VRAYLAR, and then periodically during treatment with VRAYLAR.
- weight gain. You and your healthcare provider should check your weight before you start and often during treatment with VRAYLAR.

- Low white blood cell count. Your healthcare provider may do blood tests during the first few months of treatment with VRAYLAR.
- Decreased blood pressure (orthostatic hypotension). You may feel lightheaded or faint when you rise too quickly from a sitting or lying position.
- Falls. VRAYLAR may make you sleepy or dizzy, may cause a decrease in your blood pressure when changing position (orthostatic hypotension), and can slow your thinking and motor skills which may lead to falls that can cause fractures or other injuries.
- Seizures (convulsions).
- Sleepiness, drowsiness, feeling tired, difficulty thinking and doing normal activities. See “What should I avoid while taking VRAYLAR?”
- Problems controlling your body temperature so that you feel too warm. See “What should I avoid while taking VRAYLAR?”
- Difficulty swallowing that can cause food or liquid to get into your lungs.

The most common side effects of VRAYLAR include: difficulty moving or slow movements, tremors, uncontrolled body movements, restlessness and feeling like you need to move around, sleepiness, nausea, vomiting, indigestion, constipation, feeling tired, trouble sleeping, increased appetite, and dizziness
These are not all the possible side effects of VRAYLAR.
Call your doctor for medical advice about side effects. You may report side effects to FDA at 1-800-FDA-1088.

How should I store VRAYLAR?

- Store VRAYLAR at room temperature, between 68°F to 77°F (20°C to 25°C).
- Protect 3 mg and 4.5 mg capsules from light to help prevent potential color fading.

Keep VRAYLAR and all medicines out of the reach of children.

General information about the safe and effective use of VRAYLAR.
Medicines are sometimes prescribed for purposes other than those listed in a Medication Guide. Do not use VRAYLAR for a condition for which it was not prescribed. Do not give VRAYLAR to other people, even if they have the same symptoms that you have. It may harm them. You can ask your pharmacist or healthcare provider for information about VRAYLAR that is written for health professionals.

What are the ingredients in VRAYLAR?
Active ingredient: cariprazine
Inactive ingredients: gelatin, magnesium stearate, pregelatinized starch, shellac, and titanium dioxide.
Colorants include: black iron oxide, FD&C Blue 1, FD&C Red 3, FD&C Red 40, or yellow iron oxide.
Manufactured by: Forest Laboratories Ireland Limited, Dublin, IE.
Distributed by: AbbVie Inc. North Chicago, IL 60064, USA
©2025 AbbVie. All rights reserved.
VRAYLAR and its design are trademarks of Allergan Pharmaceuticals International Limited, an AbbVie company.
For more information, go to www.VRAYLAR.com or call 1-800-678-1605.

This Medication Guide has been approved by the U.S. Food and Drug Administration. Revised 12/2025

20093086

PRINCIPAL DISPLAY PANEL

NDC 61874-115-20
Rx Only
Vraylar®
(cariprazine) capsules
1.5 mg per capsule
ATTENTION PRESCRIBER: PLEASE DISPENSE
MEDICATION GUIDE TO EACH PATIENT.
Each capsule contains cariprazine HCl equivalent to
1.5 mg cariprazine base.
20 capsules (2x10-count blister cards).

PRINCIPAL DISPLAY PANEL

NDC 61874-130-20
Rx Only
Vraylar®
(cariprazine) capsules
3 mg per capsule
ATTENTION PRESCRIBER: PLEASE DISPENSE
MEDICATION GUIDE TO EACH PATIENT.
Each capsule contains cariprazine HCl equivalent to
3 mg cariprazine base.
20 capsules (2x10-count blister cards)

PRINCIPAL DISPLAY PANEL

NDC 61874-145-30
Rx Only
Vraylar®
(cariprazine) capsules
4.5 mg per capsule
ATTENTION PRESCRIBER: PLEASE
DISPENSE MEDICATION GUIDE
TO EACH PATIENT.
30 Capsules

PRINCIPAL DISPLAY PANEL

NDC 61874-160-30
Rx Only
Vraylar®
(cariprazine) capsules
6 mg per capsule
ATTENTION PRESCRIBER: PLEASE
DISPENSE MEDICATION GUIDE
TO EACH PATIENT.
30 Capsules

PRINCIPAL DISPLAY PANEL

NDC 61874-250-30
Rx Only
Vraylar®
(cariprazine) capsules
0.5 mg per capsule
Dispense the accompanying

Medication Guide to each patient.
30 Capsules

PRINCIPAL DISPLAY PANEL

NDC 61874-275-30
Rx Only
Vraylar®
(cariprazine) capsules
0.75 mg per capsule
Dispense the accompanying

Medication Guide to each patient.
30 Capsules

PRINCIPAL DISPLAY PANEL

NDC 61874-170-08
Rx Only

Vraylar®